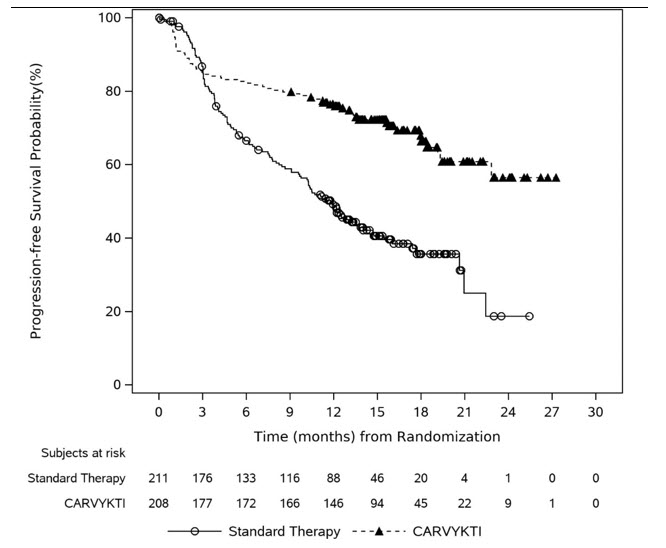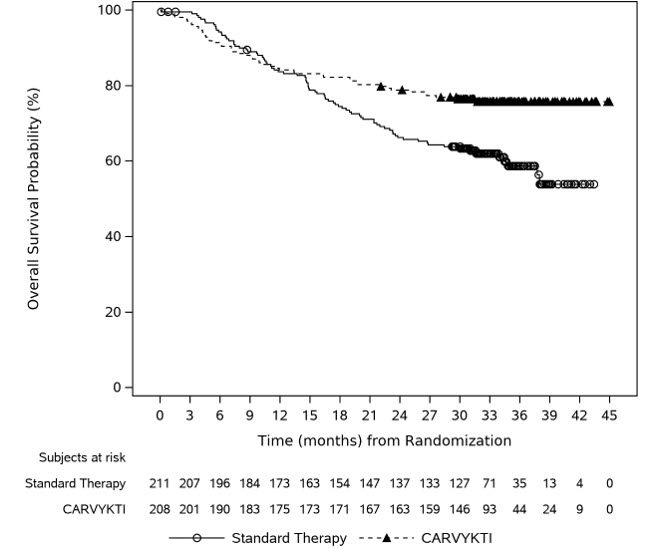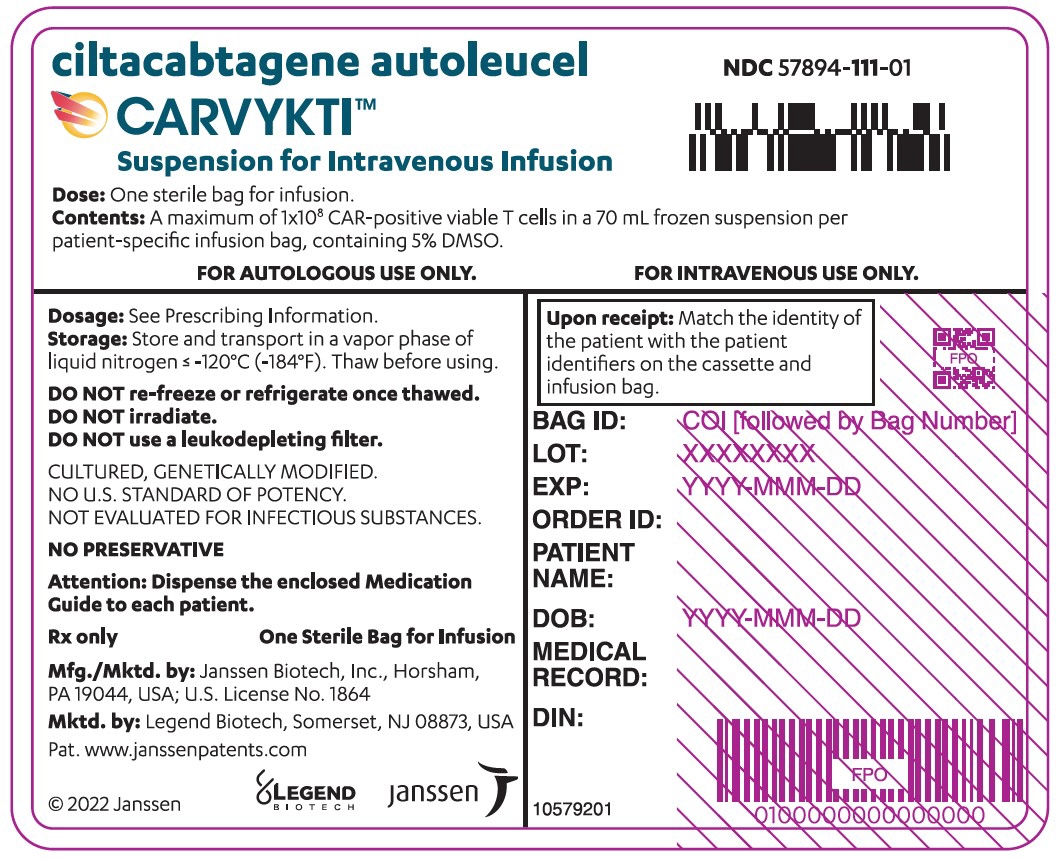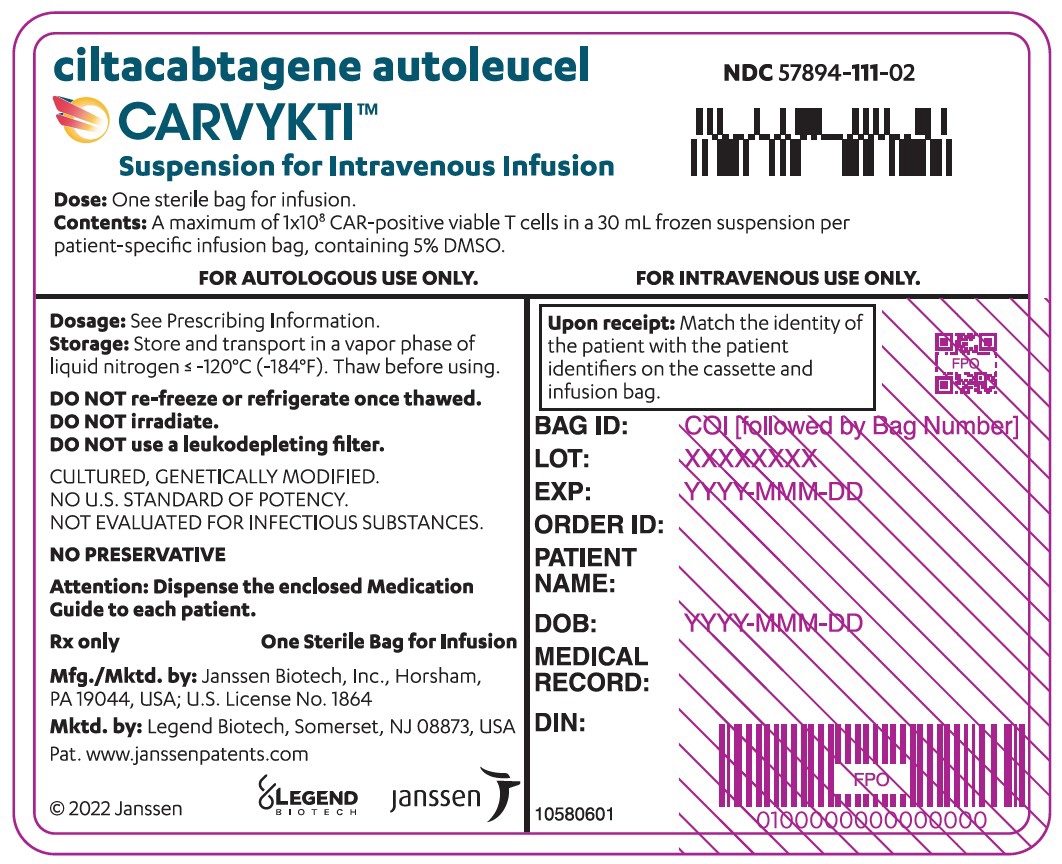 DRUG LABEL: CARVYKTI
NDC: 57894-111 | Form: INJECTION, SUSPENSION
Manufacturer: Janssen Biotech, Inc
Category: other | Type: CELLULAR THERAPY
Date: 20251016

ACTIVE INGREDIENTS: CILTACABTAGENE AUTOLEUCEL 100000000 1/1 1
INACTIVE INGREDIENTS: DIMETHYL SULFOXIDE

HIGHLIGHTS OF PRESCRIBING INFORMATION

These highlights do not include all the information needed to use CARVYKTI safely and effectively. See full prescribing information for CARVYKTI.
CARVYKTI®(ciltacabtagene autoleucel) suspension for intravenous infusion
Initial U.S. Approval: 2022

WARNING: CYTOKINE RELEASE SYNDROME, NEUROLOGIC TOXICITIES, HLH/MAS, PROLONGED and RECURRENT CYTOPENIA, and SECONDARY HEMATOLOGICAL MALIGNANCIES

See full prescribing information for complete boxed warning.

- Cytokine Release Syndrome (CRS), including fatal or life-threatening reactions, occurred in patients following treatment with CARVYKTI. Do not administer CARVYKTI to patients with active infection or inflammatory disorders. Treat severe or life-threatening CRS with tocilizumab or tocilizumab and corticosteroids. (2.2, 2.3, 5.2)
- Immune Effector Cell-Associated Neurotoxicity Syndrome (ICANS), which may be fatal or life-threatening, occurred following treatment with CARVYKTI, including before CRS onset, concurrently with CRS, after CRS resolution, or in the absence of CRS. Monitor for neurologic events after treatment with CARVYKTI. Provide supportive care and/or corticosteroids as needed. (2.2, 2.3, 5.3)
- Parkinsonism and Guillain-Barré syndrome and their associated complications resulting in fatal or life-threatening reactions have occurred following treatment with CARVYKTI. (5.3)
- Hemophagocytic Lymphohistiocytosis/Macrophage Activation Syndrome (HLH/MAS), including fatal and life-threatening reactions, occurred in patients following treatment with CARVYKTI. HLH/MAS can occur with CRS or neurologic toxicities. (5.4)
- Prolonged and/or recurrent cytopenias with bleeding and infection and requirement for stem cell transplantation for hematopoietic recovery occurred following treatment with CARVYKTI. (5.5)
- Immune Effector Cell-associated Enterocolitis (IEC-EC), including fatal or life-threatening reactions, occurred following treatment with CARVYKTI. (5.9)
- Secondary hematological malignancies, including myelodysplastic syndrome and acute myeloid leukemia, have occurred following treatment with CARVYKTI. T-cell malignancies have occurred following treatment of hematologic malignancies with BCMA- and CD19-directed genetically modified autologous T-cell immunotherapies, including CARVYKTI. (5.10)

RECENT MAJOR CHANGES

Boxed Warnings | 10/2025
Dosage and Administration (2.2, 2.3) | 06/2025
Warnings and Precautions (5.2, 5.3) | 06/2025
Warnings and Precautions, CARVYKTI REMS (5.5) Removed | 06/2025
Warnings and Precautions, Effects on Ability to Drive and Use Machines (5.11) Removed | 06/2025
Warnings and Precautions (5.6, 5.9) | 10/2025

1 INDICATIONS AND USAGE

CARVYKTI is a B-cell maturation antigen (BCMA)-directed genetically modified autologous T cell immunotherapy indicated for the treatment of adult patients with relapsed or refractory multiple myeloma who have received at least 1 prior line of therapy, including a proteasome inhibitor and an immunomodulatory agent, and are refractory to lenalidomide. (1)

2 DOSAGE AND ADMINISTRATION

For autologous use only. For intravenous use only.

- Administer a lymphodepleting regimen of cyclophosphamide and fludarabine before infusion of CARVYKTI. (2.2)
- Do NOT use a leukodepleting filter. (2.2)
- Verify the patient's identity prior to infusion. (2.2)
- Premedicate with acetaminophen and an H1-antihistamine. (2.2)
- Avoid prophylactic use of systemic corticosteroids. (2.2)
- Confirm availability of tocilizumab prior to infusion. (2.2, 5.2)
- Dosing of CARVYKTI is based on the number of chimeric antigen receptor (CAR)-positive viable T cells. (2.1)
- Recommended dose range is 0.5–1.0×10^6CAR-positive viable T cells per kg of body weight, with a maximum dose of 1×10^8CAR-positive viable T cells per single-dose infusion. (2.1)

3 DOSAGE FORMS AND STRENGTHS

- CARVYKTI is a cell suspension for intravenous infusion. (3)
- A single dose of CARVYKTI contains a cell suspension of 0.5–1.0×10^6CAR-positive viable T cells per kg body weight in one infusion bag. (3)

4 CONTRAINDICATIONS

None (4)

5 WARNINGS AND PRECAUTIONS

- Prolonged and Recurrent Cytopenias: Patients may exhibit ≥Grade 3 cytopenias following CARVYKTI infusion. One or more recurrences of Grade 3 or higher cytopenias may occur after partial or complete recovery of cytopenias. Monitor blood counts prior to and after CARVYKTI infusion. Prolonged neutropenia has been associated with increased risk of infection. (5.5)
- Infections: Monitor patients for signs and symptoms of infection; treat appropriately. (5.6)
- Hypogammaglobulinemia: Monitor and consider immunoglobulin replacement therapy. (5.7)
- Hypersensitivity Reactions: Hypersensitivity reactions have occurred. Monitor for hypersensitivity reactions during infusion. (5.8)
- Immune Effector Cell-associated Enterocolitis:Patients may exhibit prolonged and severe diarrhea in the months following CARVYKTI infusion. Monitor for signs and symptoms of IEC-Enterocolitis after CARVYKTI infusion and manage per institutional guidelines. (5.9)
- Secondary Malignancies: Secondary hematological malignancies, including myelodysplastic syndrome and acute myeloid leukemia, have occurred. T-cell malignancies have occurred following treatment of hematologic malignancies with BCMA- and CD19-directed genetically modified autologous T-cell immunotherapies, including CARVYKTI. In the event that a secondary malignancy occurs after treatment with CARVYKTI, contact Janssen Biotech, Inc. at 1-800-526-7736. (5.10)

6 ADVERSE REACTIONS

The most common nonlaboratory adverse reactions (incidence greater than 20%) are pyrexia, cytokine release syndrome, hypogammaglobulinemia, hypotension, musculoskeletal pain, fatigue, infections-pathogen unspecified, cough, chills, diarrhea, nausea, encephalopathy, decreased appetite, upper respiratory tract infection, headache, tachycardia, dizziness, dyspnea, edema, viral infections, coagulopathy, constipation, and vomiting. The most common Grade 3 or 4 laboratory adverse reactions (incidence greater than or equal to 50%) include lymphopenia, neutropenia, white blood cell decreased, thrombocytopenia, and anemia. (6)

To report SUSPECTED ADVERSE REACTIONS, contact Janssen Biotech, Inc. at 1-800-526-7736 (1-800-JANSSEN) or FDA at 1-800-FDA-1088 or www.fda.gov/medwatch

FULL PRESCRIBING INFORMATION

WARNING: CYTOKINE RELEASE SYNDROME, NEUROLOGIC TOXICITIES, HLH/MAS, PROLONGED and RECURRENT CYTOPENIA, and SECONDARY HEMATOLOGICAL MALIGNANCIES

Cytokine Release Syndrome (CRS), including fatal or life-threatening reactions, occurred in patients following treatment with CARVYKTI. Do not administer CARVYKTI to patients with active infection or inflammatory disorders. Treat severe or life-threatening CRS with tocilizumab or tocilizumab and corticosteroids [see Dosage and Administration (2.2, 2.3), Warnings and Precautions (5.2)] .

Immune Effector Cell-Associated Neurotoxicity Syndrome (ICANS), which may be fatal or life-threatening, occurred following treatment with CARVYKTI, including before CRS onset, concurrently with CRS, after CRS resolution, or in the absence of CRS. Monitor for neurologic events after treatment with CARVYKTI. Provide supportive care and/or corticosteroids as needed [see Dosage and Administration (2.2, 2.3), Warnings and Precautions (5.3)] .

Parkinsonism and Guillain-Barré syndrome (GBS) and their associated complications resulting in fatal or life-threatening reactions have occurred following treatment with CARVYKTI [see Warnings and Precautions (5.3)] .

Hemophagocytic Lymphohistiocytosis/Macrophage Activation Syndrome (HLH/MAS), including fatal and life-threatening reactions, occurred in patients following treatment with CARVYKTI. HLH/MAS can occur with CRS or neurologic toxicities [see Warnings and Precautions (5.4)].

Prolonged and/or recurrent cytopenias with bleeding and infection and requirement for stem cell transplantation for hematopoietic recovery occurred following treatment with CARVYKTI [see Warnings and Precautions (5.5)] .

Immune Effector Cell-associated Enterocolitis (IEC-EC), including fatal or life-threatening reactions, occurred following treatment with CARVYKTI [see Warnings and Precautions (5.9)].

Secondary hematological malignancies, including myelodysplastic syndrome and acute myeloid leukemia, have occurred in patients following treatment with CARVYKTI. T-cell malignancies have occurred following treatment of hematologic malignancies with BCMA- and CD19-directed genetically modified autologous T-cell immunotherapies, including CARVYKTI [see Warnings and Precautions (5.10)] .

1 INDICATIONS AND USAGE

CARVYKTI is indicated for the treatment of adult patients with relapsed or refractory multiple myeloma, who have received at least 1 prior line of therapy, including a proteasome inhibitor and an immunomodulatory agent, and are refractory to lenalidomide.

2 DOSAGE AND ADMINISTRATION

2.1 Dose

CARVYKTI is provided as a single dose for infusion containing a suspension of chimeric antigen receptor (CAR)-positive viable T cells in one infusion bag.

The recommended dose range is 0.5–1.0×10^6CAR-positive viable T cells per kg of body weight, with a maximum dose of 1×10^8CAR-positive viable T cells per single infusion.

2.2 Administration

CARVYKTI is for autologous use only. For intravenous use only.The patient's identity must match the patient identifiers on the CARVYKTI cassette and infusion bag. Do not infuse CARVYKTI if the information on the patient-specific labels does not match the intended patient.

Preparing the Patient for CARVYKTI Infusion

Confirm availability of CARVYKTI prior to starting the lymphodepleting chemotherapy regimen.

Pretreatment

Administer the lymphodepleting chemotherapy regimen: cyclophosphamide 300 mg/m^2intravenously (IV) and fludarabine 30 mg/m^2IV daily for 3 days.

See the prescribing information of cyclophosphamide and fludarabine for information on dose adjustment in renal impairment.

Lymphodepleting regimen must be delayed if a patient has serious adverse reactions from preceding bridging therapies (including clinically significant active infection, cardiac toxicity, and pulmonary toxicity) or active graft versus host disease in patient with prior allogeneic stem cell transplant. Consider repeating lymphodepleting regimen if CARVYKTI dosing is delayed by more than 14 days and patient has recovered from toxicity of the first lymphodepleting regimen.

Administer CARVYKTI infusion 2 to 4 days after the completion of the lymphodepleting chemotherapy regimen.

CARVYKTI infusion should be delayed if a patient has any of the following conditions:

- Clinically significant active infection or inflammatory disorders.
- Grade ≥3 non-hematologic toxicities of cyclophosphamide and fludarabine conditioning, except for Grade 3 nausea, vomiting, diarrhea, or constipation. CARVYKTI infusion should be delayed until resolution of these events to Grade ≤1.

Premedication

Administer the following pre-infusion medications to all patients 30 – 60 minutes prior to CARVYKTI infusion:

- Antipyretics (oral or intravenous acetaminophen 650 to 1000 mg).
- Antihistamine (oral or intravenous diphenhydramine 25 to 50 mg or equivalent).

Avoid prophylactic use of systemic corticosteroids because their use may interfere with the activity of CARVYKTI.

Receipt of CARVYKTI

- All sites approved for infusion will support required storage conditions for vapor phase of liquid nitrogen.
- CARVYKTI is shipped directly to the cell laboratory or clinical pharmacy associated with the infusion center in the vapor phase of a liquid nitrogen shipper.
- Confirm the patient's identity with the patient identifiers on the shipper.
- If the patient is not expected to be ready for same-day administration, before the shipper expires, transfer CARVYKTI to onsite vapor phase of liquid nitrogen storage.

Preparation of CARVYKTI for Infusion

Do not thaw the product until it is ready to be used. Coordinate the timing of CARVYKTI thaw and infusion. Confirm the infusion time in advance and adjust the start time for thaw so that CARVYKTI is available for infusion when the patient is ready. Once thawed, the CARVYKTI infusion must be completed within 2.5 hours at room/ambient temperature (20 °C to 25 °C).

Prior to thawing the product, confirm that tocilizumab and emergency equipment are available prior to the infusion and during the recovery period.

1. Confirm patient identity: Prior to CARVYKTI preparation, match the patient's identity with the patient identifiers on the CARVYKTI cassette. Do not remove the CARVYKTI infusion bag from the cassette if the information on the patient-specific label does not match the intended patient. Contact Janssen Biotech, Inc. at 1-800-526-7736 if there are any discrepancies between the labels and the patient identifiers.
2. Once patient identification is confirmed, remove the CARVYKTI product bag from the cassette and check that the patient information on the cassette label matches the patient information on the bag label.
3. Inspect the product bag for any breaches of container integrity, such as breaks or cracks before and after thawing. Do not administer if the bag is compromised, and contact Janssen Biotech, Inc. at 1-800-526-7736.
4. Place the infusion bag inside a sealable plastic bag (preferably sterile) prior to thawing.
5. Thaw CARVYKTI at 37 °C±2 °C using either a water bath or dry thaw method until there is no visible ice in the infusion bag. Total time from start of thaw until completion of thawing should be no more than 15 minutes.
6. Remove the infusion bag from the sealable plastic bag and wipe dry. Gently mix the contents of the bag to disperse clumps of cellular material. If visible cell clumps remain, continue to gently mix the contents of the bag. Small clumps of cellular material should disperse with gentle manual mixing. Do not pre-filter into a different container, wash, spin down, or resuspend CARVYKTI in new media prior to infusion.
7. Do not re-freeze or refrigerate thawed product.

Administration

- For autologous infusion only.
- Do NOT use a leukocyte-depleting filter.
- Confirm that a minimum of two doses of tocilizumab and emergency equipment are available prior to infusion and during the recovery period.
- Central venous access may be utilized for the infusion of CARVYKTI and is encouraged in patients with poor peripheral access.

1. Confirm the patient's identity with the patient identifiers on the infusion bag. Do not infuse CARVYKTI if the information on the patient-specific label does not match the intended patient.
2. Prime the tubing of the infusion set with normal saline prior to infusion.
3. Once thawed, administer the entire contents of the CARVYKTI bag by intravenous infusion within 2.5 hours using infusion sets fitted with an in-line filter.
4. Gently mix the contents of the bag during CARVYKTI infusion to disperse cell clumps.
5. After the entire content of the product bag is infused, flush the administration line, inclusive of the in-line filter, with normal saline with a volume equal or greater to the total hold up volume of the primary administration set used inclusive of the drip tube, to ensure that all product is delivered.

CARVYKTI contains human blood cells that are genetically modified with replication-incompetent, self-inactivating, lentiviral vector. Follow universal precautions and local biosafety guidelines for handling and disposal of CARVYKTI to avoid potential transmission of infectious diseases.

Monitoring After Infusion

Monitor patients at least daily for 7 days following CARVYKTI infusion for signs and symptoms of cytokine release syndrome (CRS) and neurologic toxicities.

Instruct patients to remain within proximity of a healthcare facility for at least 2 weeks following infusion. Advise patients to avoid driving for at least 2 weeks following infusion.

2.3 Management of Severe Adverse Reactions

Cytokine Release Syndrome (CRS)

Identify CRS based on clinical presentation [see Warnings and Precautions (5.2)] . Evaluate for and treat other causes of fever, hypoxia and hypotension. Consider laboratory testing to monitor for disseminated intravascular coagulation, hematology parameters, as well as pulmonary, cardiac, renal, and hepatic function. If CRS is suspected, manage according to the recommendations in Table 1. Physicians may also consider management per current practice guidelines.

Patients who experience CRS should be closely monitored for cardiac and other organ function until resolution of symptoms. Consider anti-seizure prophylaxis with levetiracetam in patients who experience CRS.

Patients who experience Grade 2 or higher CRS (e.g., hypotension not responsive to fluids, or hypoxia requiring supplemental oxygenation) should be monitored with continuous telemetry and pulse oximetry.

For severe or life-threatening CRS, consider intensive care unit level monitoring and supportive therapy.

For CRS refractory to first line interventions such as tocilizumab or tocilizumab and corticosteroids, consider alternate treatment options (i.e., higher corticosteroid dose, alternative anti-cytokine agents, e.g., anti-IL1 and/or anti-TNFα, anti-T cell therapies). Refractory CRS is characterized by fevers, end-organ toxicity (e.g., hypoxia, hypotension) not improving within 12 hours of first line interventions or development of HLH/MAS.

If concurrent neurologic toxicity is suspected during CRS, administer:

- Corticosteroids according to the more aggressive intervention based on the CRS and neurologic toxicity grades in Tables 1 and 2
- Tocilizumab according to the CRS grade in Table 1
- Anti-seizure medication according to the neurologic toxicity in Table 2

Table 1: CRS grading and management guidance
CRS Grade [Based on ASTCT 2019 grading system (Lee et.al, 2019), modified to include organ toxicity.] | Tocilizumab [Refer to tocilizumab prescribing information for details.] / Corticosteroids [Continue corticosteroids use until the event is Grade 1 or less; taper steroids if total corticosteroid exposure is greater than 3 days.]
Grade 1
Temperature ≥38 °C [Attributed to CRS. Fever may not always be present concurrently with hypotension or hypoxia, as it may be masked by interventions such as antipyretics or anti-cytokine therapy (e.g., tocilizumab or steroids). Absence of fever does not impact CRS management decision. In this case, CRS management is driven by hypotension and/or hypoxia and by the more severe symptom not attributable to any other cause.] | In patients with:; - Early onset of fever (if onset less than 72 hours after infusion); Tocilizumab 8 mg/kg intravenously (IV) over 1 hour (not to exceed 800 mg) may be considered. Corticosteroids: N/A
Grade 2
Symptoms require and respond to moderate intervention. Temperature ≥38 °C with: Hypotension not requiring vasopressors, and/or, Hypoxia requiring oxygen via cannula or blow-by, or, Grade 2 organ toxicity. [Organ toxicity grading based on National Cancer Institute Common Terminology Criteria for Adverse Events (NCI CTCAE) version 5.0.] | Administer tocilizumab 8 mg/kg IV over 1 hour (not to exceed 800 mg). Repeat tocilizumab every 8 hours as needed if not responsive to intravenous fluids up to 1 liter or increasing supplemental oxygen. Consider dexamethasone 10 mg IV every 12–24 hours. If no improvement within 24 hours or rapid progression, repeat tocilizumab and escalate dose and frequency of dexamethasone (20 mg IV every 6 to 12 hours). If no improvement within 24 hours or continued rapid progression, switch to methylprednisolone 2 mg/kg IV every 12 hours. After 2 doses of tocilizumab, consider alternative anti-cytokine agents [Monoclonal antibodies targeting cytokines may be considered based on institutional practice for unresponsive CRS.] . Do not exceed 3 doses of tocilizumab in 24 hours, or 4 doses in total.
Grade 3
Symptoms require and respond to aggressive intervention. Temperature ≥38 °C with: Hypotension requiring one vasopressor with or without vasopressin, and/or, Hypoxia requiring oxygen via high-flow nasal cannula [Low-flow nasal cannula is ≤6 L/min; high-flow nasal cannula is >6 L/min.] , facemask, non-rebreather mask, or Venturi mask, or, Grade 3 organ toxicity or Grade 4 transaminitis. | Administer tocilizumab 8 mg/kg IV over 1 hour (not to exceed 800 mg). Repeat tocilizumab every 8 hours as needed if not responsive to intravenous fluids up to 1 liter or increasing supplemental oxygen. Consider dexamethasone 10 mg IV every 12 hours. If no improvement within 24 hours or rapid progression, repeat tocilizumab and escalate dose and frequency of dexamethasone (20 mg IV every 6 to 12 hours). If no improvement within 24 hours or continued rapid progression, switch to methylprednisolone 2 mg/kg IV every 12 hours. After 2 doses of tocilizumab, consider alternative anti-cytokine agents. Do not exceed 3 doses of tocilizumab in 24 hours, or 4 doses in total.
Grade 4
Life-threatening symptoms. Requirements for ventilator support, continuous veno-venous hemodialysis (CVVHD). Temperature ≥38 °C with: Hypotension requiring multiple vasopressors (excluding vasopressin), and/or, Hypoxia requiring positive pressure (e.g., CPAP, BiPAP, intubation, and mechanical ventilation), or, Grade 4 organ toxicity (excluding transaminitis). | Administer tocilizumab 8 mg/kg IV over 1 hour (not to exceed 800 mg). Repeat tocilizumab every 8 hours as needed if not responsive to intravenous fluids up to 1 liter or increasing supplemental oxygen. Administer dexamethasone 20 mg IV every 6 hours. After 2 doses of tocilizumab, consider alternative anti-cytokine agents . Do not exceed 3 doses of tocilizumab in 24 hours, or 4 doses in total. If no improvement within 24 hours, consider methylprednisolone (1–2 g IV, repeat every 24 hours if needed; taper as clinically indicated) or other immunosuppressants (e.g. other anti-T cell therapies).

Neurologic Toxicities

Monitor patients for signs and symptoms of neurologic toxicities (ICANS and other neurologic toxicities) (Table 2). Rule out other causes of neurologic signs or symptoms. Provide intensive care and supportive therapy for severe or life-threatening neurologic toxicities. Please see section 5.3for non ICANS neurologic toxicities. If ICANS is suspected, manage according to the recommendations in Table 2. Physicians may also consider management per current practice guidelines.

If concurrent CRS is suspected during the neurologic toxicity event, administer:

- Corticosteroids according to the more aggressive intervention based on the CRS and neurologic toxicity grades in Tables 1 and 2
- Tocilizumab according to CRS grade in Table 1
- Anti-seizure medication according to neurologic toxicity in Table 2

Table 2: Guideline for management of ICANS
ICANS Grade [ASTCT 2019 criteria for grading Neurologic Toxicity (Lee et.al, 2019).] | Corticosteroids
Grade 1 ICE score 7–9 [If patient is arousable and able to perform Immune Effector Cell-Associated Encephalopathy (ICE) Assessment, assess: Orientation (oriented to year, month, city, hospital = 4 points); Naming (name 3 objects, e.g., point to clock, pen, button = 3 points); Following Commands (e.g., "show me 2 fingers" or "close your eyes and stick out your tongue" = 1 point); Writing (ability to write a standard sentence = 1 point); and Attention (count backwards from 100 by ten = 1 point). If patient is unarousable and unable to perform ICE Assessment (Grade 4 ICANS) = 0 points.] or depressed level of consciousness: awakens spontaneously. | Consider dexamethasone [All references to dexamethasone administration are dexamethasone or equivalent.] 10 mg IV every 12 to 24 hours for 2 to 3 days. Consider non-sedating, anti-seizure medicines (e.g., levetiracetam) for seizure prophylaxis.
Grade 2 ICE score-3–6 or depressed level of consciousness: awakens to voice | Administer dexamethasone 10 mg IV every 12 hours for 2–3 days, or longer for persistent symptoms. Consider steroid taper if total corticosteroid exposure is greater than 3 days. If no improvement after 24 hours or worsening of neurologic toxicity, increase the dose and/or frequency of dexamethasone up to a maximum of 20 mg IV every 6 hours. Consider non-sedating, anti-seizure medicines (e.g., levetiracetam) for seizure prophylaxis.
Grade 3 ICE score-0–2 (If ICE score is 0, but the patient is arousable (e.g., awake with global aphasia) and able to perform assessment) or depressed level of consciousness: awakens only to tactile stimulus, or seizures, either:; - any clinical seizure, focal or generalized, that resolves rapidly, or - non-convulsive seizures on EEG that resolve with intervention,; or raised intracranial pressure (ICP): focal/local edema on neuroimaging [Intracranial hemorrhage with or without associated edema is not considered a neurotoxicity feature and is excluded from ICANS grading. It may be graded according to NCI CTCAE v5.0.] . | Administer dexamethasone 10 mg–20 mg IV every 6 hours. If no improvement after 24 hours or worsening of neurologic toxicity, escalate dexamethasone dose to at least 20 mg IV every 6 hours, OR escalate to high-dose methylprednisolone (1–2 g/day, repeat every 24 hours if needed; taper as clinically indicated) Consider non-sedating, anti-seizure medicines (e.g., levetiracetam) for seizure prophylaxis. If cerebral edema is suspected, consider hyperventilation and hyperosmolar therapy. Give high-dose methylprednisolone (1–2 g, repeat every 24 hours if needed; taper as clinically indicated).
Grade 4 ICE score-0 (Patient is unarousable and unable to perform ICE assessment) or depressed level of consciousness either:; - patient is unarousable or requires vigorous or repetitive tactile stimuli to arouse, or - stupor or coma,; or seizures, either:; - life-threatening prolonged seizure (>5 min), or - repetitive clinical or electrical seizures without return to baseline in between,; or motor findings [Tremors and myoclonus associated with immune effector cell therapies may be graded according to NCI CTCAE v5.0, but they do not influence ICANS grading.] :; - deep focal motor weakness such as hemiparesis or paraparesis,; or raised ICP/cerebral edema, with signs/symptoms such as:; - diffuse cerebral edema on neuroimaging, or - decerebrate or decorticate posturing, or - cranial nerve VI palsy, or - papilledema, or - Cushing's triad | Administer dexamethasone 20 mg IV every 6 hours. If no improvement after 24 hours or worsening of neurologic toxicity, escalate to high-dose methylprednisolone (1–2 g/day, repeated every 24 hours if needed; taper as clinically indicated). Consider non-sedating, anti-seizure medicines (e.g., levetiracetam) for seizure prophylaxis. If raised ICP/cerebral edema is suspected, consider hyperventilation and hyperosmolar therapy. Give high-dose methylprednisolone (1–2 g/day, repeat every 24 hours if needed; taper as clinically indicated), and consider neurology and/or neurosurgery consultation.
Note: ICANS grade and management is determined by the most severe event (ICE score, level of consciousness, seizure, motor findings, raised ICP/cerebral edema), not attributable to any other cause.

3 DOSAGE FORMS AND STRENGTHS

CARVYKTI is a cell suspension for intravenous infusion.

A single dose of CARVYKTI contains a cell suspension of 0.5–1.0×10^6CAR-positive viable T cells per kg body weight in one infusion bag up to a maximum of 1×10^8CAR-positive viable T cells [see How Supplied/Storage and Handling (16)] .

4 CONTRAINDICATIONS

None.

5 WARNINGS AND PRECAUTIONS

5.1 Increased Early Mortality

In CARTITUDE-4, a randomized (1:1), controlled trial, there was a numerically higher percentage of early deaths in patients randomized to the CARVYKTI treatment arm compared to the control arm. Among patients with deaths occurring within the first 10 months from randomization, a greater proportion (29/208; 14%) occurred in the CARVYKTI arm compared to (25/211; 12%) in the control arm [see Clinical Studies (14)]. Of the 29 deaths that occurred in the CARVYKTI arm within the first 10 months of randomization, 10 deaths occurred prior to CARVYKTI infusion, and 19 deaths occurred after CARVYKTI infusion. Of the 10 deaths that occurred prior to CARVYKTI infusion, all occurred due to disease progression, and none occurred due to adverse events. Of the 19 deaths that occurred after CARVYKTI infusion, 3 occurred due to disease progression, and 16 occurred due to adverse events. The most common adverse events were due to infection (n=12).

5.2 Cytokine Release Syndrome

Cytokine release syndrome (CRS), including fatal or life-threatening reactions, occurred following treatment with CARVYKTI. Among patients receiving CARVYKTI for relapsed or refractory multiple myeloma in the CARTITUDE-1 and CARTITUDE-4 studies (N=285), CRS occurred in 84% (238/285), including ≥ Grade 3 CRS (ASTCT 2019) in 4% (11/285) of patients. The median time to onset of CRS, any grade, was 7 days (range: 1 to 23 days). Cytokine release syndrome resolved in 82% with a median duration of 4 days (range: 1 to 97 days). The most common manifestations of CRS in all patients combined (≥ 10%) included fever (84%), hypotension (29%) and aspartate aminotransferase increased (11%). Serious events that may be associated with CRS include pyrexia, hemophagocytic lymphohistiocytosis, respiratory failure, disseminated intravascular coagulation, capillary leak syndrome, and supraventricular and ventricular tachycardia [see Adverse Reactions (6.1)].

Cytokine release syndrome occurred in 78% of patients in CARTITUDE-4 (3% Grade 3 to 4) and in 95% of patients in CARTITUDE-1 (4% Grade 3 to 4).

Identify CRS based on clinical presentation. Evaluate for and treat other causes of fever, hypoxia, and hypotension. CRS has been reported to be associated with findings of HLH/MAS, and the physiology of the syndromes may overlap. HLH/MAS is a potentially life-threatening condition. In patients with progressive symptoms of CRS or refractory CRS despite treatment, evaluate for evidence of HLH/MAS [see Warnings and Precautions (5.4)].

Confirm that a minimum of two doses of tocilizumab are available prior to infusion of CARVYKTI.

Of the 285 patients who received CARVYKTI in clinical trials, 53% (150/285) patients received tocilizumab; 35% (100/285) received a single dose, while 18% (50/285) received more than 1 dose of tocilizumab. Overall, 14% (39/285) of patients received at least one dose of corticosteroids for treatment of CRS.

Monitor patients at least daily for 7 days following CARVYKTI infusion for signs and symptoms of CRS. Monitor patients for signs or symptoms of CRS for at least 2 weeks after infusion. At the first sign of CRS, immediately institute treatment with supportive care, tocilizumab, or tocilizumab and corticosteroids, as indicated in Table 1 [see Dosage and Administration (2.3)] .

Counsel patients to seek immediate medical attention should signs or symptoms of CRS occur at any time [see Patient Counseling Information (17)].

5.3 Neurologic Toxicities

Neurologic toxicities, which may be severe, life-threatening or fatal, occurred following treatment with CARVYKTI. Neurologic toxicities included ICANS, neurologic toxicity with signs and symptoms of parkinsonism, GBS, immune mediated myelitis, peripheral neuropathies and cranial nerve palsies. Counsel patients on the signs and symptoms of these neurologic toxicities, and on the delayed nature of onset of some of these toxicities. Instruct patients to seek immediate medical attention for further assessment and management if signs or symptoms of any of these neurologic toxicities occur at any time [see Patient Counseling Information (17)] .

Among patients receiving CARVYKTI in the CARTITUDE-1 and CARTITUDE-4 studies for relapsed and refractory multiple myeloma, one or more neurologic toxicities occurred in 24% (69/285), including ≥ Grade 3 cases in 7% (19/285) of patients. The median time to onset was 10 days (range: 1 to 101) with 63/69 (91%) of cases developing by 30 days. Neurologic toxicities resolved in 72% (50/69) of patients with a median duration to resolution of 23 days (range: 1 to 544). Of patients developing neurotoxicity, 96% (66/69) also developed CRS. Subtypes of neurologic toxicities included ICANS in 13%, peripheral neuropathy in 7%, cranial nerve palsy in 7%, parkinsonism in 3%, and immune mediated myelitis in 0.4% of the patients [see Adverse Reactions (6.1)] .

Immune Effector Cell-associated Neurotoxicity Syndrome (ICANS)

Patients receiving CARVYKTI may experience fatal or life-threatening ICANS following treatment with CARVYKTI, including before CRS onset, concurrently with CRS, after CRS resolution, or in the absence of CRS.

Among patients receiving CARVYKTI in the CARTITUDE-1 and CARTITUDE-4 studies, ICANS occurred in 13% (36/285), including Grade ≥ 3 in 2% (6/285) of the patients. The median time to onset of ICANS was 8 days (range: 1 to 28 days). ICANS resolved in 30 of 36 (83%) of patients with a median time to resolution of 3 days (range: 1 to 143 days). The median duration of ICANS was 6 days (range: 1 to 1229 days) in all patients including those with ongoing neurologic events at the time of death or data cut off. Of patients with ICANS 97% (35/36) had CRS. The onset of ICANS occurred during CRS in 69% of patients, before and after the onset of CRS in 14% of patients respectively.

Immune Effector Cell-associated Neurotoxicity Syndrome occurred in 7% of patients in CARTITUDE-4 (0.5% Grade 3) and in 23% of patients in CARTITUDE-1 (3% Grade 3).

The most frequent ≥2% manifestations of ICANS included encephalopathy (12%), aphasia (4%), headache (3%), motor dysfunction (3%), ataxia (2%) and sleep disorder (2%) [see Adverse Reactions (6.1)] .

Monitor patients at least daily for 7 days following CARVYKTI infusion for signs and symptoms of ICANS. Rule out other causes of ICANS symptoms. Monitor patients for signs or symptoms of ICANS for at least 2 weeks after infusion and treat promptly. Neurologic toxicity should be managed with supportive care and/or corticosteroids as needed [see Dosage and Administration (2.3)] . Advise patients to avoid driving for at least 2 weeks following infusion.

Parkinsonism

Neurologic toxicity with parkinsonism has been reported in clinical trials of CARVYKTI.

Among patients receiving CARVYKTI in the CARTITUDE-1 and CARTITUDE-4 studies, parkinsonism occurred in 3% (8/285), including Grade ≥ 3 in 2% (5/285) of the patients. The median time to onset of parkinsonism was 56 days (range: 14 to 914 days). Parkinsonism resolved in 1 of 8 (13%) of patients with a median time to resolution of 523 days. The median duration of parkinsonism was 243.5 days (range: 62 to 720 days) in all patients including those with ongoing neurologic events at the time of death or data cut off. The onset of parkinsonism occurred after CRS for all patients and after ICANS for 6 patients.

Parkinsonism occurred in 1% of patients in CARTITUDE-4 (no Grade 3 to 4) and in 6% of patients in CARTITUDE-1 (4% Grade 3 to 4).

The manifestations of parkinsonism included movement disorders, cognitive impairment, and personality changes [see Adverse Reactions (6.1)] .

Monitor patients for signs and symptoms of parkinsonism that may be delayed in onset and managed with supportive care measures. There is limited efficacy information with medications used for the treatment of Parkinson's disease for the improvement or resolution of parkinsonism symptoms following CARVYKTI treatment.

Guillain-Barré Syndrome

A fatal outcome following GBS occurred following treatment with CARVYKTI despite treatment with intravenous immunoglobulins. Symptoms reported include those consistent with Miller-Fisher variant of GBS, encephalopathy, motor weakness, speech disturbances, and polyradiculoneuritis.

Monitor for GBS. Evaluate patients presenting with peripheral neuropathy for GBS. Consider treatment of GBS with supportive care measures and in conjunction with immunoglobulins and plasma exchange, depending on severity of GBS.

Immune Mediated Myelitis

Grade 3 myelitis occurred 25 days following treatment with CARVYKTI in CARTITUDE-4 in a patient who received CARVYKTI as subsequent therapy. Symptoms reported included hypoesthesia of the lower extremities and the lower abdomen with impaired sphincter control. Symptoms improved with the use of corticosteroids and intravenous immune globulin. Myelitis was ongoing at the time of death from other cause [see Adverse Reactions (6.1)] .

Peripheral Neuropathy

Peripheral neuropathy occurred following treatment with CARVYKTI.

Among patients receiving CARVYKTI in the CARTITUDE-1 and CARTITUDE-4 studies, peripheral neuropathy occurred in 7% (21/285), including Grade ≥ 3 in 1% (3/285) of the patients. The median time to onset of peripheral neuropathy was 57 days (range: 1 to 914 days). Peripheral neuropathy resolved in 11 of 21 (52%) of patients with a median time to resolution of 58 days (range: 1 to 215 days). The median duration of peripheral neuropathy was 149.5 days (range: 1 to 692 days) in all patients including those with ongoing neurologic events at the time of death or data cut off [see Adverse Reactions (6.1)] .

Peripheral neuropathies occurred in 7% of patients in CARTITUDE-4 (0.5% Grade 3 to 4) and in 7% of patients in CARTITUDE-1 (2% Grade 3 to 4).

Monitor patients for signs and symptoms of peripheral neuropathies.

Patients who experience peripheral neuropathy may also experience cranial nerve palsies or GBS.

Cranial Nerve Palsies

Cranial nerve palsies occurred following treatment with CARVYKTI.

Among patients receiving CARVYKTI in the CARTITUDE-1 and CARTITUDE-4 studies, cranial nerve palsies occurred in 7% (19/285), including Grade ≥ 3 in 1% (1/285) of the patients. The median time to onset of cranial nerve palsies was 21 days (range: 17 to 101 days). Cranial nerve palsies resolved in 17 of 19 (89%) of patients with a median time to resolution of 66 days (range: 1 to 209 days). The median duration of cranial nerve palsies was 70 days (range: 1 to 262 days) in all patients including those with ongoing neurologic events at the time of death or data cut off [see Adverse Reactions (6.1)] .

Cranial nerve palsies occurred in 9% of patients in CARTITUDE-4 (1% Grade 3 to 4) and in 3% of patients in CARTITUDE-1 (1% Grade 3 to 4).

The most frequent cranial nerve affected was the 7thcranial nerve. Additionally, cranial nerves III, V, and VI have been reported to be affected.

Monitor patients for signs and symptoms of cranial nerve palsies. Consider management with systemic corticosteroids, depending on the severity and progression of signs and symptoms.

5.4 Hemophagocytic Lymphohistiocytosis (HLH)/Macrophage Activation Syndrome (MAS)

Among patients receiving CARVYKTI in the CARTITUDE-1 and CARTITUDE-4 studies, HLH/MAS occurred in 1% (3/285) of patients. All events of HLH/MAS had onset within 99 days of receiving CARVYKTI, with a median onset of 10 days (range: 8 to 99 days) and all occurred in the setting of ongoing or worsening CRS. The manifestations of HLH/MAS included hyperferritinemia, hypotension, hypoxia with diffuse alveolar damage, coagulopathy and hemorrhage, cytopenia and multi-organ dysfunction, including renal dysfunction and respiratory failure.

Patients who develop HLH/MAS have an increased risk of severe bleeding. Monitor hematologic parameters in patients with HLH/MAS and transfuse per institutional guidelines. Fatal cases of HLH/MAS occurred following treatment with CARVYKTI [see Adverse Reactions (6.1)].

HLH is a life-threatening condition with a high mortality rate if not recognized and treated early. Treatment of HLH/MAS should be administered per institutional standards.

5.5 Prolonged and Recurrent Cytopenias

Patients may exhibit prolonged and recurrent cytopenias following lymphodepleting chemotherapy and CARVYKTI infusion.

Among patients receiving CARVYKTI in the CARTITUDE-1 and CARTITUDE-4 studies, Grade 3 or higher cytopenias not resolved by day 30 following CARVYKTI infusion occurred in 62% (176/285) of the patients and included thrombocytopenia 33% (94/285), neutropenia 27% (76/285), lymphopenia 24% (67/285) and anemia 2% (6/285). After Day 60 following CARVYKTI infusion 22%, 20%, 5%, and 6% of patients had a recurrence of Grade 3 or 4 lymphopenia, neutropenia, thrombocytopenia, and anemia respectively, after initial recovery of their Grade 3 or 4 cytopenia. Seventy-seven percent (219/285) of patients had one, two or three or more recurrences of Grade 3 or 4 cytopenias after initial recovery of Grade 3 or 4 cytopenia. Sixteen and 25 patients had Grade 3 or 4 neutropenia and thrombocytopenia, respectively, at the time of death [see Adverse Reactions (6.1)].

Monitor blood counts prior to and after CARVYKTI infusion. Manage cytopenias with growth factors and blood product transfusion support according to local institutional guidelines.

5.6 Infections

CARVYKTI should not be administered to patients with active infection or inflammatory disorders. Severe, life-threatening, or fatal infections, occurred in patients after CARVYKTI infusion.

Among patients receiving CARVYKTI in the CARTITUDE-1 and CARTITUDE-4 studies, infections occurred in 57% (163/285), including ≥ Grade 3 in 24% (69/285) of patients. Grade 3 or 4 infections with an unspecified pathogen occurred in 12%, viral infections in 6%, bacterial infections in 5%, and fungal infections in 1% of patients. Overall, 5% (13/285) of patients had Grade 5 infections, 2.5% of which were due to COVID-19. Patients treated with CARVYKTI had an increased rate of fatal COVID-19 infections compared to the standard therapy arm [see Adverse Reactions (6.1)].

Monitor patients for signs and symptoms of infection before and after CARVYKTI infusion and treat patients appropriately. Administer prophylactic, pre-emptive and/or therapeutic antimicrobials according to the standard institutional guidelines. Febrile neutropenia was observed in 5% of patients after CARVYKTI infusion and may be concurrent with CRS. In the event of febrile neutropenia, evaluate for infection and manage with broad-spectrum antibiotics, fluids and other supportive care, as medically indicated.

Counsel patients on the importance of prevention measures. Follow institutional guidelines for the vaccination and management of immunocompromised patients with COVID-19.

Viral Reactivation

Hepatitis B virus (HBV) reactivation, in some cases resulting in fulminant hepatitis, hepatic failure and death, can occur in patients with hypogammaglobulinemia.

Perform screening for Cytomegalovirus (CMV), HBV, hepatitis C virus (HCV), and human immunodeficiency virus (HIV) or any other infectious agents if clinically indicated in accordance with clinical guidelines before collection of cells for manufacturing.

Consider antiviral therapy to prevent viral reactivation per local institutional guidelines/clinical practice.

Reactivation of John Cunningham (JC) virus, leading to progressive multifocal leukoencephalopathy (PML), including cases with fatal outcomes, have been reported following treatment with CARVYKTI [see Adverse Reactions (6.2)]. Perform appropriate diagnostic evaluations in patients with neurological adverse events.

5.7 Hypogammaglobulinemia

Hypogammaglobulinemia can occur in patients receiving treatment with CARVYKTI.

Among patients receiving CARVYKTI in the CARTITUDE-1 and CARTITUDE-4 studies, hypogammaglobulinemia adverse event was reported in 36% (102/285) of patients; laboratory IgG levels fell below 500 mg/dL after infusion in 93% (265/285) of patients. Hypogammaglobulinemia either as an adverse reaction or laboratory IgG level below 500 mg/dL, after infusion occurred in 94% (267/285) of patients treated. Fifty six percent (161/285) of patients received intravenous immunoglobulin (IVIG) post CARVYKTI for either an adverse reaction or prophylaxis [see Adverse Reactions (6.1)] .

Monitor immunoglobulin levels after treatment with CARVYKTI and administer IVIG for IgG <400 mg/dL. Manage per local institutional guidelines, including infection precautions and antibiotic or antiviral prophylaxis.

Use of Live Vaccines

The safety of immunization with live viral vaccines during or following CARVYKTI treatment has not been studied. Vaccination with live virus vaccines is not recommended for at least 6 weeks prior to the start of lymphodepleting chemotherapy, during CARVYKTI treatment, and until immune recovery following treatment with CARVYKTI.

5.8 Hypersensitivity Reactions

Hypersensitivity reactions occurred following treatment with CARVYKTI.

Among patients receiving CARVYKTI in the CARTITUDE-1 and CARTITUDE-4 studies, hypersensitivity reactions occurred in 5% (13/285), all of which were ≤ Grade 2. Manifestations of hypersensitivity reactions included flushing, chest discomfort, tachycardia, wheezing, tremor, burning sensation, non-cardiac chest pain, and pyrexia.

Serious hypersensitivity reactions, including anaphylaxis, may be due to the dimethyl sulfoxide (DMSO) in CARVYKTI. Patients should be carefully monitored for 2 hours after infusion for signs and symptoms of severe reaction. Treat promptly and manage patients appropriately according to the severity of the hypersensitivity reaction.

5.9 Immune Effector Cell-associated Enterocolitis

Immune effector cell-associated enterocolitis (IEC-EC) has occurred in patients treated with CARVYKTI [see Adverse Reactions (6.2)]. Manifestations include severe or prolonged diarrhea, abdominal pain and weight loss requiring parenteral nutrition. IEC-EC has been associated with fatal outcome from perforation or sepsis. Manage according to institutional guidelines including referral to gastroenterology and infectious disease specialists.

In cases of refractory IEC-EC, consider additional workup to exclude alternative etiologies, including T-cell lymphoma of the GI tract, which has been reported in the postmarketing setting [see Warnings and Precautions (5.10)and Adverse Reactions (6.2)].

5.10 Secondary Malignancies

Patients treated with CARVYKTI may develop secondary malignancies.

Among patients receiving CARVYKTI in the CARTITUDE-1 and CARTITUDE-4 studies, myeloid neoplasms occurred in 5% (13/285) of patients (9 cases of myelodysplastic syndrome, 3 cases of acute myeloid leukemia, and 1 case of myelodysplastic syndrome followed by acute myeloid leukemia). The median time to onset of myeloid neoplasms was 447 days (range: 56 to 870 days) after treatment with CARVYKTI. Ten of these 13 patients died following the development of myeloid neoplasms; 2 of the 13 cases of myeloid neoplasm occurred after initiation of subsequent antimyeloma therapy. Cases of myelodysplastic syndrome and acute myeloid leukemia have also been reported in the post marketing setting.

T-cell malignancies have occurred following treatment of hematologic malignancies with BCMA- and CD19-directed genetically modified autologous T-cell immunotherapies, including CARVYKTI. Mature T-cell malignancies, including CAR-positive tumors, may present as soon as weeks following infusions, and may include fatal outcomes [see Boxed Warning, Adverse Reactions (6.1, 6.2)] .

Monitor life-long for secondary malignancies. In the event that a secondary malignancy occurs, contact Janssen Biotech, Inc. at 1-800-526-7736 for reporting and to obtain instructions on collection of patient samples.

6 ADVERSE REACTIONS

6.1 Clinical Trials Experience

Because clinical trials are conducted under widely varying conditions, adverse reaction rates observed in the clinical trials of a drug cannot be directly compared to rates in the clinical trials of another drug and may not reflect the rates observed in practice.

The safety data described in the WARNINGS and PRECAUTIONS section reflect exposure to CARVYKTI in 285 patients with relapsed or refractory multiple myeloma: one randomized, open-label with 188 patients in CARTITUDE-4 and one single-arm, open-label study with 97 patients in CARTITUDE-1.

CARTITUDE-4

The safety of CARVYKTI was evaluated in CARTITUDE-4, a randomized, open-label multicenter study, in which patients with relapsed and lenalidomide refractory multiple myeloma received CARVYKTI meeting the product specifications (N=188) or standard therapy (N=211) [see Clinical Studies (14)] . Patients with known active or prior history of central nervous system involvement, patients who exhibit clinical signs of meningeal involvement of multiple myeloma and patients with a history of Parkinson's disease or other neurodegenerative disorder, were excluded from the trial. Patients received CARVYKTI at a median dose of 0.71×10^6CAR-positive viable T-cells/kg (range: 0.41 to 1.08×10^6cells/kg). The median age of the 188 participants was 62 years (range: 27 to 78 years); 40% were 65 years or older, and 57% were male; 76% were White, were 9% Hispanic or Latino, 8% were Asian, and 3% were Black.

The Eastern Cooperative Oncology Group (ECOG) performance status at baseline was 0 in 56%, 1 in 44%. For the details about the study population, see Clinical Studies (14).

The most common nonlaboratory adverse reactions (≥20%) included pyrexia, CRS, hypogammaglobulinemia, musculoskeletal pain, fatigue, upper respiratory tract infection, diarrhea, viral infections, headache, hypotension, and nausea.

Serious adverse reactions occurred in 34% of patients. The most common nonlaboratory serious adverse reactions (≥5%) were pneumonia (9%), viral infection (6%), CRS (6%), and cranial nerve palsies (5%).

Table 3 summarizes the adverse reactions that occurred in at least 10% of patients treated with CARVYKTI.

Table 3: Adverse reactions observed in at least 10% of patients treated with CARVYKTI (N=188) and standard therapy (N=208) in CARTITUDE-4
 | CARVYKTI N=188 | CARVYKTI N=188 | Standard Therapy N=208 | Standard Therapy N=208
System Organ Class (SOC) Preferred term | Any Grade (%) | Grade 3 or higher (%) | Any Grade (%) | Grade 3 or higher (%)
Gastrointestinal disorders | - | - | - | -
Diarrhea [Diarrhea includes Colitis, and Diarrhea.] | 27 | 3 | 27 | 2
Nausea | 20 | 0 | 18 | 1
Constipation | 10 | 0 | 21 | 1
General disorders and administrative site conditions | - | - | - | -
Pyrexia | 79 | 5 | 16 | 1
Fatigue [Represents multiple related terms.] | 28 | 3 | 50 | 3
Edema [Edema includes Face edema, Generalized edema, Localized edema, Edema peripheral, Periorbital edema, Peripheral swelling, Pulmonary edema, and Scrotal edema.] | 11 | 1 | 20 | 1
Pain | 10 | 1 | 14 | <1
Immune system disorders | - | - | - | -
Hypogammaglobulinemia [Hypogammaglobulinemia includes subjects with adverse event of hypogammaglobulinemia and/or laboratory IgG levels that fell below 500 mg/dL following CARVYKTI infusion or standard therapy.] | 94 | 9 | 72 | <1
Cytokine release syndrome | 78 | 3 | <1 | 0
Infections and infestations | - | - | - | -
Upper respiratory tract infection | 25 | 1 | 40 | 5
Viral infection | 23 | 4 | 31 | 6
Bacterial infection | 15 | 6 | 17 | 4
Pneumonia | 14 | 9 | 18 | 11
Metabolism and nutrition disorders | - | - | - | -
Decreased appetite | 10 | 0 | 5 | 0
Musculoskeletal and connective tissue disorders | - | - | - | -
Musculoskeletal pain | 34 | 2 | 47 | 4
Nervous system disorders | - | - | - | -
Headache | 23 | 0 | 13 | 0
Encephalopathy [Encephalopathy includes Amnesia, Bradyphrenia, Confusional state, Depressed level of consciousness, Disturbance in attention, Immune effector cell-associated neurotoxicity syndrome, Lethargy, and Psychomotor retardation.] | 11 | 2 | 4 | 1
Respiratory, thoracic and mediastinal disorders | - | - | - | -
Cough | 15 | 0 | 18 | 0
Hypoxia | 12 | 3 | 1 | 1
Vascular disorders | - | - | - | -
Hypotension | 23 | 4 | 3 | 0

Other clinically important adverse reactions that occurred in less than 10% of patients treated with CARVYKTI include the following:

- Blood and lymphatic system disorders: coagulopathy [Represents multiple related terms.] (5%), febrile neutropenia (2%), lymphocytosis (2%)
- Cardiac disorders: tachycardia (5%), cardiac arrhythmias(3%)
- Gastrointestinal disorders: abdominal pain (6%), vomiting (5%)
- General disorders and administration site conditions: chills (6%)
- Immune system disorders:HLH (1%)
- Infections and infestations:gastroenteritis (7%), sepsis (9%), urinary tract infection (5%), fungal infection (3%)
- Investigations: c-reactive protein increased (6%)
- Metabolism and nutrition disorders: hypophosphatemia (10%), hyperferritinemia (7%)
- Neoplasms benign, malignant, and unspecified (incl cysts and polyps): hematologic malignancy [Hematologic malignancy includes Myelodysplastic syndrome, Acute myeloid leukaemia and T-cell lymphoma] (3%)
- Nervous system disorders: dizziness (9%), cranial nerve palsies (9%), motor dysfunction [Motor dysfunction includes Bradykinesia, Coordination abnormal, Dysgraphia, Extrapyramidal disorder, Micrographia, Muscle spasms, Muscular weakness, and Parkinsonism] (9%), peripheral neuropathy (7%), sleep disorder (6%), tremor (4%), aphasia (3%), ataxia (3%)
- Psychiatric disorders: delirium (2%), personality changes (2%)
- Renal and urinary disorders: renal failure (5%)
- Respiratory, thoracic and mediastinal disorders: dyspnea (10%)
- Skin and subcutaneous tissues: rash (7%)
- Vascular disorders: hemorrhage (9%), hypertension (7%), thrombosis (3%), capillary leak syndrome (1%)

Laboratory Abnormalities

Table 4 presents the most common Grade 3 or 4 laboratory abnormalities based on laboratory data, occurring in at least 10% of patients.

Table 4: Grade 3 or 4 laboratory abnormalities in at least 10% of patients treated with CARVYKTI (N=188) and standard therapy (N=208) in CARTITUDE-4
 | CARVYKTI (N=188) | Standard Therapy (N=208)
Laboratory Abnormality | Grade 3 or 4 (%) | Grade 3 or 4 (%)
Lymphocyte count decreased | 99 | 62
Neutrophil count decreased | 95 | 88
White blood cell decreased | 94 | 69
Platelet count decreased | 47 | 20
Hemoglobin decreased | 34 | 17
Laboratory abnormalities graded using NCI Common Terminology Criteria for Adverse Events version 5.0. Laboratory abnormalities are sorted by decreasing frequency in the Grade column.

Other clinically important Grade 3 or 4 laboratory abnormalities (based on laboratory data) that occurred in less than 10% of patients treated with CARVYKTI include gamma glutamyl transferase increased, fibrinogen decreased, aspartate aminotransferase increased, hypokalemia, alanine aminotransferase increased, hyponatremia, alkaline phosphatase increased, hypertriglyceridemia, hypomagnesemia, hypoalbuminemia, hypocalcemia, and blood bilirubin increased.

CARTITUDE-1

The safety data described in this section reflect the exposure of 97 adult patients with relapsed/refractory multiple myeloma in the CARTITUDE-1 study (USA cohort) to CARVYKTI and includes 17 patients (18%) with manufacturing failures either because they received CARVYKTI that did not meet product release specifications or there were insufficient data to confirm product release specifications for CARVYKTI. Patients received CARVYKTI across a dose range of 0.51 to 0.95×10^6CAR-positive viable T cells/kg body weight [see Clinical Studies (14)] . Patients with a history of CNS disease (such as seizure or cerebrovascular ischemia) or requiring ongoing treatment with chronic immunosuppression were excluded. The median duration of follow-up was 18 months. The median age of the study population was 61 years (range: 43 to 78 years); 36% were 65 years or older, and 59% were men. The Eastern Cooperative Oncology Group (ECOG) performance status at baseline was 0 in 40%, 1 in 56%, and 2 in 4% of patients. Three of the patients treated with CARVYKTI had a creatinine clearance of <45 mL/min at baseline. For the details about the study population, see Clinical Studies (14).

The most common (greater or equal to 10%) Grade 3 or higher nonlaboratory adverse reactions were infections-pathogen unspecified (19%), pneumonia (13%), hematologic malignancy (10%) and hypotension (10%).

The most common nonlaboratory adverse reactions (incidence greater than or equal to 20%) included pyrexia, CRS, hypogammaglobulinemia, hypotension, musculoskeletal pain, fatigue, infections of unspecified pathogen, cough, chills, diarrhea, nausea, encephalopathy, decreased appetite, upper respiratory tract infection, headache, tachycardia, dizziness, dyspnea, edema, viral infections, coagulopathy, constipation, and vomiting.

Serious adverse reactions occurred in 55% of patients. The most common non-laboratory (greater than or equal to 5%) serious adverse reactions included CRS (21%), sepsis (7%), encephalopathy (10%), and pneumonia (8%). Fatal adverse reactions occurred in 9% of patients.

Table 5 summarizes the adverse reactions that occurred in at least 10% of patients treated with CARVYKTI.

Table 5: Adverse reactions observed in at least 10% of patients treated with CARVYKTI in CARTITUDE-1 (N=97)
System Organ Class (SOC) Preferred term | Any Grade (%) | Grade 3 or higher (%)
Blood and lymphatic system disorders | - | -
Coagulopathy [Coagulopathy includes Activated partial thromboplastin time prolonged, Coagulopathy, Disseminated intravascular coagulation, Hypofibrinogenemia, International normalized ratio increased, and Prothrombin time prolonged.] | 22 | 2
Febrile Neutropenia | 10 | 9
Cardiac disorders | - | -
Tachycardia [Represents multiple related terms] | 27 | 1
Gastrointestinal disorders | - | -
Diarrhea [Diarrhea includes Colitis and Diarrhea.] | 33 | 1
Nausea | 31 | 1
Constipation | 22 | 0
Vomiting | 20 | 0
General disorders and administrative site conditions | - | -
Pyrexia | 96 | 5
Fatigue | 47 | 7
Chills | 33 | 0
Edema [Edema includes Face edema, Generalized edema, Localized edema, Edema peripheral, Periorbital edema, Peripheral swelling, Pulmonary edema, and Scrotal edema.] | 23 | 0
Immune system disorders | - | -
Cytokine release syndrome | 95 | 5
Hypogammaglobulinemia [Hypogammaglobulinemia includes subjects with adverse event of hypogammaglobulinemia and/or laboratory IgG levels that fell below 500 mg/dL following CARVYKTI infusion.] | 93 | 2
Infections and infestations | - | -
Infections-pathogen unspecified | 41 | 19
Upper respiratory tract infection | 28 | 3
Viral infections | 23 | 7
Pneumonia | 14 | 13
Sepsis | 10 | 7
Metabolism and nutrition disorders | - | -
Decreased appetite | 29 | 1
Musculoskeletal and connective tissue disorders | - | -
Musculoskeletal pain | 48 | 2
Nervous system disorders | - | -
Encephalopathy [Encephalopathy includes Amnesia, Bradyphrenia, Confusional state, Depressed level of consciousness, Disturbance in attention, Encephalopathy, Immune effector cell-associated neurotoxicity syndrome, Lethargy, Memory impairment, Mental impairment, Mental status changes, Noninfective encephalitis, and Somnolence.] | 30 | 6
Headache | 27 | 0
Dizziness | 23 | 1
Motor dysfunction [Motor dysfunction includes Motor dysfunction, Muscle spasms, Muscle tightness, Muscular weakness, and Myoclonus.] | 16 | 3
Psychiatric disorders | - | -
Insomnia | 13 | 0
Respiratory, thoracic and mediastinal disorders | - | -
Cough | 39 | 0
Dyspnea [Dyspnea includes Acute respiratory failure, Dyspnea, Dyspnea exertional, Respiratory failure, and Tachypnea.] | 23 | 3
Nasal congestion | 15 | 0
Hypoxia | 12 | 4
Neoplasms benign, malignant, and unspecified (incl cysts and polyps) | - | -
Hematologic malignancy [Hematologic malignancy includes Myelodysplastic syndrome and Acute myeloid leukemia.] | 10 | 10
Vascular disorders | - | -
Hypotension | 51 | 10
Hypertension | 19 | 6
Hemorrhage [Hemorrhage includes Conjunctival hemorrhage, Contusion, Ecchymosis, Epistaxis, Eye contusion, Hematochezia, Hemoptysis, Infusion site hematoma, Oral contusion, Petechiae, Post procedural hemorrhage, Pulmonary hemorrhage, Retinal hemorrhage, and Subdural hematoma.] | 16 | 4

Other clinically important adverse reactions that occurred in less than 10% of patients treated with CARVYKTI include the following:

- Cardiac disorders: cardiac arrhythmias [Represents multiple related terms] (8%), chest pain (7%)
- Eye disorders: diplopia (1%)
- Gastrointestinal disorders: dysphagia (1%)
- Immune system disorders:HLH (1%), hypersensitivity reaction (5%)
- Infections and Infestations:bacterial infections (9%), urinary tract infection (4.1%)
- Injury, Poisoning and Procedural complications: fall (3.1%)
- Metabolism and Nutrition Disorders: tumor lysis syndrome (1%)
- Musculoskeletal and Connective tissue disorders: posture abnormal (1%)
- Nervous system disorders: aphasia (8%), ataxia (8%), peripheral neuropathy (7%), tremor (6%), parkinsonism (4.1%), micrographia (4.1%), dysgraphia (3.1%), reduced facial expression (3.1%), cranial nerve palsies (3.1%), bradykinesia (2.1%), paresis (1%), cogwheel rigidity (1%), cerebrovascular accident (1%), seizure (1%), slow speech (1%), nystagmus (1%)
- Psychiatric disorders: delirium (5%), depression (4.1%), psychomotor retardation (1%)
- Renal and urinary disorders: renal failure (7%)
- Skin and subcutaneous tissues: rash (8%)
- Vascular Disorders: thrombosis (5%)

Laboratory Abnormalities

Table 6 presents the most common Grade 3 or 4 laboratory abnormalities based on laboratory data, occurring in at least 10% of patients.

Table 6: Grade 3 or 4 laboratory abnormalities in at least 10% of patients treated with CARVYKTI in CARTITUDE-1 (N=97)
Laboratory Abnormality | Grade 3 or 4 (%)
Lymphopenia | 99
Neutropenia | 98
White blood cell decreased | 98
Anemia | 72
Thrombocytopenia | 63
Aspartate aminotransferase increased | 21
Laboratory abnormalities graded using NCI Common Terminology Criteria for Adverse Events version 5.0. Laboratory abnormalities are sorted by decreasing frequency in the Grade column.

Other clinically important Grade 3 or 4 laboratory abnormalities (based on laboratory data) that occurred in less than 10% of patients treated with CARVYKTI include the following: fibrinogen decreased, hypoalbuminemia, alanine aminotransferase increased, hyponatremia, hypocalcemia, gamma glutamyl transferase increased, alkaline phosphatase increased, hypokalemia, blood bilirubin increased.

6.2 Postmarketing Experience

Because adverse events to marketed products are reported voluntarily from a population of uncertain size, it is not always possible to reliably estimate their frequency or establish a causal relationship to product exposure.

The following adverse events have been identified during postmarketing use of CARVYKTI.

Neoplasms:T cell malignancies including T-cell lymphoma of the gastrointestinal tract (including fatal cases).

Gastrointestinal disorders:immune effector cell-associated enterocolitis and gastrointestinal perforation (including fatal cases) [see Warnings and Precautions (5.9)] .

Immune System disorders:infusion related reactions.

Infections and infestations:John Cunningham (JC) virus progressive multifocal leukoencephalopathy (including fatal cases) [see Warnings and Precautions (5.6)].

7 DRUG INTERACTIONS

HIV and the lentivirus used to make CARVYKTI have limited, short spans of identical genetic material (RNA). Therefore, some commercial HIV nucleic acid tests (NATs) may yield false-positive results in patients who have received CARVYKTI.

8 USE IN SPECIFIC POPULATIONS

8.1 Pregnancy

Risk Summary

There are no available data on the use of CARVYKTI in pregnant women. No reproductive and developmental toxicity studies in animals have been conducted with CARVYKTI to assess whether it can cause fetal harm when administered to a pregnant woman. It is not known whether CARVYKTI has the potential to be transferred to the fetus and cause fetal toxicity. Based on the mechanism of action, if the transduced cells cross the placenta, they may cause fetal toxicity, including B-cell lymphocytopenia and hypogammaglobulinemia. Therefore, CARVYKTI is not recommended for women who are pregnant, or for women of childbearing potential not using contraception. Pregnant women should be advised that there may be risks to the fetus. Pregnancy after CARVYKTI therapy should be discussed with the treating physician.

In the U.S. general population, the estimated background risk of major birth defects and miscarriage in clinically recognized pregnancies is 2%–4% and 15%–20%, respectively.

8.2 Lactation

Risk Summary

There is no information regarding the presence of CARVYKTI in human milk, the effect on the breastfed infant, and the effects on milk production. The developmental and health benefits of breastfeeding should be considered along with the mother's clinical need for CARVYKTI and any potential adverse effects on the breastfed infant from CARVYKTI or from the underlying maternal condition.

8.3 Females and Males of Reproductive Potential

Pregnancy Testing

Pregnancy status for females of child-bearing age should be verified prior to starting treatment with CARVYKTI.

Contraception

There are insufficient data to provide a recommendation concerning duration of contraception following treatment with CARVYKTI.

In clinical trials, female patients of childbearing potential were advised to practice a highly effective method of contraception and male patients with partners of childbearing potential or whose partners were pregnant were instructed to use a barrier method of contraception, until one year after the patient has received CARVYKTI infusion.

See the prescribing information for lymphodepleting chemotherapy for information on the need for contraception in patients who receive the lymphodepleting chemotherapy.

Infertility

There are no data on the effect of CARVYKTI on fertility.

8.4 Pediatric Use

Safety and effectiveness of CARVYKTI in pediatric patients have not been established.

8.5 Geriatric Use

Of the 97 patients in CARTITUDE-1 that received CARVYKTI, 28% were 65 to 75 years of age, and 8% were 75 years of age or older. CARTITUDE-1 did not include sufficient numbers of patients aged 65 and older to determine whether the effectiveness differs compared with that of younger patients. In 62 patients less than 65 years of age, all grade and Grade 3 and higher neurologic toxicities occurred in 19% (12/62) and 6% (4/62), respectively. Of the 35 patients ≥65 years of age, all grade and Grade 3 and higher neurologic toxicities occurred in 37% (13/35) and 20% (7/35), respectively.

Of the 188 patients in CARTITUDE-4 that received CARVYKTI, 38% were 65 to 75 years of age, and 2% were 75 years of age or older. In 112 patients less than 65 years of age, all grade and Grade 3 and higher neurologic toxicities occurred in 16% (18/112) and 3% (3/112) respectively. Of the 76 patients ≥65 years of age, all grade and Grade 3 and higher neurologic toxicities occurred in 34% (26/76) and 7% (5/76) respectively.

11 DESCRIPTION

CARVYKTI®(ciltacabtagene autoleucel) is a BCMA-directed genetically modified autologous T cell immunotherapy. CARVYKTI is prepared from the patient's peripheral blood mononuclear cells, which are obtained via a standard leukapheresis procedure. The mononuclear cells are enriched for T cells and genetically modified ex vivo by transduction with a replication-incompetent lentiviral vector to express a CAR comprising an anti-BCMA targeting domain, which consists of two single-domain antibodies linked to a 4-1BB costimulatory domain and a CD3-zeta signaling domain.

The transduced anti-BCMA CAR T cells are expanded in cell culture, washed, formulated into a suspension and cryopreserved. The product must pass a sterility test before release for shipping as a frozen suspension in a patient-specific infusion bag. The product is thawed and then infused back into the patient, where the anti-BCMA CAR T cells can recognize and eliminate BCMA-expressing target cells [see Dosage and Administration (2.2), How Supplied/Storage and Handling (16)].

In addition to T cells, CARVYKTI may contain Natural Killer (NK) cells. The formulation contains 5% dimethyl sulfoxide (DMSO).

12 CLINICAL PHARMACOLOGY

12.1 Mechanism of Action

CARVYKTI is a BCMA-directed, genetically modified autologous T cell immunotherapy, which involves reprogramming a patient's own T cells with a transgene encoding a CAR that identifies and eliminates cells that express BCMA. The CARVYKTI CAR protein features two BCMA-targeting single-domain antibodies designed to confer high avidity against human BCMA, a 4-1BB co-stimulatory domain and a CD3-zeta (CD3ζ) signaling cytoplasmic domain. Upon binding to BCMA-expressing cells, the CAR promotes T cell activation, expansion, and elimination of target cells.

12.2 Pharmacodynamics

After a single infusion of CARVYKTI, expansion of CAR-positive T cells coincided with decreases of serum soluble BCMA, serum M-protein, and/or free light chains. Across all patients, levels of IL-6, IL-10, IFN-γ and IL-2 receptor alpha increased post-infusion and peaked at Days 7–14. The serum levels of all cytokines generally returned to baseline levels within 2–3 months post-infusion.

12.3 Pharmacokinetics

The pharmacokinetics (PK) of CARVYKTI was assessed in 285 adult patients with relapsed or refractory multiple myeloma in CARTITUDE-1 and CARTITUDE-4 receiving a single infusion at the median dose of 0.71×10^6CAR-positive viable T cells/kg (range: 0.41×10^6to 1.08×10^6cells/kg).

Following a single infusion, CARVYKTI exhibited an initial expansion phase followed by a rapid decline, and then a slower decline. However, high inter-individual variability was observed.

Table 7: Pharmacokinetic parameters of CARVYKTI in patients with multiple myeloma
Parameter | Summary Statistics | CARTITUDE-1 N=97 | CARTITUDE-4 N=188
Cmax(copies/µg genomic DNA) | Median (range), n | 47806 (7189 – 115234), 97 | 34891 (935 – 104861), 185
tmax(day) | Median (range), n | 12.7 (8.7 – 329.8), 97 | 12.8 (7.8 – 222.8), 185
AUC0–28d(copies*day/µg genomic DNA) | Median (range), n | 371569 (58691 – 2024126), 97 | 293490 (9215 – 1738455), 184
t1/2(day) | Median (range), n | 15.3 (3.0 – 95.4), 42 | 11.7 (4.1 – 179.6), 49

After the cell expansion, the persistence phase of CARVYKTI was observed for all patients. At the time of analysis in CARTITUDE-1 (n=65) and CARTITUDE-4 (n=87) studies, the median time for CAR transgene levels in peripheral blood to return to the pre-dose baseline level was approximately 100 days (range: 28 to 365 days) and 109 days (range: 29 to 366 days) post-infusion respectively.

Detectable CARVYKTI exposures in bone marrow indicate a distribution of CARVYKTI from systemic circulation to bone marrow. Similar to blood transgene levels, bone marrow transgene levels declined over time and exhibited high inter-individual variability.

Patients with higher CAR-T cell expansion tended to have higher rates of CRS. Some patients required tocilizumab, corticosteroids, and anakinra for the management of CRS. CARVYKTI continues to expand and persist following administration of tocilizumab, corticosteroids, and anakinra. In CARTITUDE-1, CARVYKTI median Cmaxand AUC0–28din patients treated with tocilizumab (n=68) for CRS were 168% and 209% of those in patients (n=29) who did not receive tocilizumab for CRS, respectively. The median Cmaxand AUC0–28dof CARVYKTI in patients who received corticosteroids (n=21) for CRS were 186% and 307% of those in patients who did not receive corticosteroids (n=76) for CRS, respectively. In addition, the median Cmaxand AUC0–28dof CARVYKTI in patients who received anakinra (n=18) for CRS were 139% and 232% of those in patients who did not receive anakinra (n=79) for CRS, respectively. In CARTITUDE-4, the results related to tocilizumab and corticosteroid were consistent with CARTITUDE-1.

Specific Populations

The pharmacokinetics of CARVYKTI (Cmaxand AUC0–28d) were not impacted by age (27 to 78 years), gender, body weight, race, mild hepatic dysfunction [(total bilirubin ≤ upper limit of normal (ULN) and aspartate aminotransferase > ULN) or (ULN < total bilirubin ≤1.5 times ULN)], mild renal dysfunction (60 mL/min ≤ creatinine clearance [CRCL] <90 mL/min) or moderate renal dysfunction (30 mL/min ≤ creatinine clearance <60 mL/min). Formal renal and hepatic impairment studies of CARVYKTI were not conducted.

12.6 Immunogenicity

The immunogenicity of CARVYKTI has been evaluated using a validated assay for the detection of binding antibodies against the extracellular portion of the anti-BCMA CAR pre-dose, and at multiple timepoints post-infusion. In CARTITUDE-1, 19 of 97 (19.6%) patients were positive for anti-product antibodies. In CARTITUDE-4, 39 of 186 patients (21%) were positive for anti-CAR antibodies.

There was no clear evidence that the observed anti-product antibodies impact CARVYKTI kinetics of initial expansion and persistence, efficacy, or safety.

13 NONCLINICAL TOXICOLOGY

13.1 Carcinogenesis, Mutagenesis, Impairment of Fertility

No genotoxicity or carcinogenicity studies have been performed with CARVYKTI as they were not indicated. In vitro studies with CARVYKTI manufactured from healthy donors and patients with multiple myeloma showed no evidence of cytokine independent growth and no preferential integration near genes associated with oncogenic transformation.

No studies have been conducted to evaluate the effects of CARVYKTI on fertility.

14 CLINICAL STUDIES

The efficacy of CARVYKTI was evaluated in two studies, CARTITUDE-4 (NCT04181827) and CARTITUDE-1 (NCT03548207), as described below.

CARTITUDE-4

Efficacy of CARVYKTI was evaluated in CARTITUDE-4, a randomized, open-label, multicenter controlled study in adult patients with relapsed and lenalidomide-refractory multiple myeloma, who previously received at least 1 prior line of therapy including a proteasome inhibitor and an immunomodulatory agent. A total of 419 patients were randomized 1:1 to receive either a sequence of apheresis, bridging therapy, lymphodepletion and CARVYKTI (n=208) or standard therapy which included daratumumab, pomalidomide and dexamethasone (DPd) or bortezomib, pomalidomide and dexamethasone (PVd) selected by physician prior to randomization based on patient's prior antimyeloma therapy (n=211). Randomization was stratified by physician's choice of treatment (DPd vs. PVd), ISS (I vs. II vs. III) and number of prior lines of therapy (1 vs. 2 or 3).

Patients with known active or prior history of central nervous system involvement, patients who exhibit clinical signs of meningeal involvement of multiple myeloma and patients with a history of Parkinson's disease or other neurodegenerative disorder, were excluded from the trial.

In the overall study population (N=419), the median age was 61 years (range: 27 to 80 years), 57% were male, 75% were White, 3% were Black or African American, 9% were Asian, and 7% were Hispanic or Latino. Most patients (94%) were International Staging System (ISS) Stage I or II. High-risk cytogenetics [presence of t(4:14), (14:16), and 17p13 del] were present in 34% of patients. Nineteen percent of patients had presence of soft tissue plasmacytoma.

Patients had received a median of 2 (range: 1 to 3) prior lines of therapy and 85% of patients had received prior autologous stem cell transplantation (ASCT). Ninety-nine percent of patients were refractory to their last line of prior therapy. Forty-seven percent were refractory to a proteasome inhibitor (PI) and 100% were refractory to an immunomodulatory agent.

All 208 patients randomized to the CARVYKTI arm underwent apheresis, twelve (6%) were not treated with CARVYKTI due to progressive disease (n=10) or death (n=2), and twenty (10%) progressed prior to infusion with CARVYKTI but were able to receive CARVYKTI as subsequent therapy. Eight (4%) patients received CAR-T positive T cells that did not meet product release specification for CARVYKTI (non-conforming product).

Patients randomized to CARVYKTI were to receive lymphodepleting chemotherapy consisting of fludarabine 30 mg/m^2/day and cyclophosphamide 300 mg/m^2/day concurrently for 3 days followed by CARVYKTI infusion 5 to 7 days after start of lymphodepleting chemotherapy. At least one cycle of DPd or PVd bridging therapy was received for disease control between leukapheresis and the start of the lymphodepleting chemotherapy.

CARVYKTI was administered as a single IV infusion 5 to 7 days after the start of a lymphodepleting chemotherapy at a median dose of 0.71×10^6CAR-positive viable T-cells/kg (range: 0.39 to 1.07×10^6cells/kg).

In the 176 patients that received CARVYKTI as study treatment, the median time from the day after receipt of apheresis material at manufacturing facility to release of product for infusion was 44 days (range: 25 to 127 days) and the median time from first apheresis to CARVYKTI infusion was 79 days (range: 45 days to 246 days).

The primary efficacy measure was progression-free survival (PFS) analyzed based on the Intent-To-Treat Analysis Set.

The efficacy results for CARTITUDE-4 study are summarized in Table 8, Figure 1 and Figure 2 below.

Table 8: Efficacy results for CARTITUDE-4
 | CARVYKTI (N=208) | Standard Therapy (N=211)
Primary Efficacy Analysis (median duration of follow up of 15.9 months) | - | -
Progression-Free Survival [Per the International Myeloma Working Group (IMWG) consensus, as assessed by IRC] | - | -
Number of events, n (%) | 65 (31.3) | 119 (56.4)
Median, months [95% CI] [Kaplan-Meier estimate] | NE [22.8, NE] | 12 [9.8, 14.0]
Hazard ratio [95% CI] [Based on a stratified Cox proportional hazards model. A hazard ratio <1 indicates an advantage for CARVYKTI Arm. For all stratified analyses, stratification was based on investigator's choice (PVd or DPd), ISS staging (I, II, III) and number of prior lines (1 vs. 2 or 3) as randomized.] | 0.41 [0.30, 0.56] | -
p-value [Stratified log-rank test] | <0.0001 | -
Complete Response or Better Rate , % [95% CI] | 74.0 [67.5, 79.9] | 22.3 [16.8, 28.5]
p-value [Stratified Cochran-Mantel-Haenszel Chi-Squared test] | <0.0001 | -
Stringent Complete Response (sCR), n (%) | 137 (65.9) | 38 (18.0)
Complete Response (CR), n (%) | 17 (8.2) | 9 (4.3)
Overall Response Rate, ORR (sCR + CR + VGPR + PR), % [95% CI] | 84.6 [79.0, 89.2] | 67.8 [61.0, 74.0]
p-value | <0.0001 | -
Very Good Partial Response (VGPR), n (%) | 16 (7.7) | 49 (23.2)
Partial Response (PR), n (%) | 6 (2.9) | 47 (22.3)
Second Interim Analysis (median duration of follow up of 33.6 months) | - | -
Overall Survival (OS) | - | -
Number of events (%) | 50 (24.0%) | 83 (39.3%)
Number of censored (%) | 158 (76.0%) | 128 (60.7%)
Kaplan-Meier estimate (months) | - | -
Median (95% CI) | NE (NE, NE) | NE (37.75, NE)
p-value | 0.001 | -
Hazard ratio (95% CI) | 0.55 (0.39, 0.79) | -
NE=not estimable; CI=confidence interval
All efficacy endpoints are analyzed based on the Intent to treat analysis set

The estimated PFS rate at 12 months was 75.9% (95% CI: 69.4%, 81.1%) in the CARVYKTI arm and 49.5% (95% CI: 42.3%, 56.3%) in the standard therapy arm.

In the CARVYKTI arm, the estimated median duration of response (DOR) has not been reached in patients who achieved PR or better or in patients who achieved CR or better. In the standard therapy arm, the estimated median DOR was 16.6 months (95% CI: 12.9, NE).

Figure 1. Kaplan-Meier Curve of PFS in CARTITUDE-4 (Intent-To-Treat Analysis Set)

Note: Intent-to-treat analysis set consists of subjects who were randomized in the study.
Data cutoff date: November 1, 2022

At the time of primary PFS analysis, the interim analysis of overall survival (OS) did not meet criteria for statistical significance. With an estimated median follow-up of 33.6 months, a prespecified second interim analysis showed a statistically significant improvement in OS in the CARVYKTI arm compared to the standard therapy arm.

A higher proportion of patients in the CARVYKTI arm compared to the standard therapy arm died within the first 10 months of randomization as shown in Figure 2.

Figure 2: Kaplan-Meier Plot of Overall Survival (Intent-to-Treat Analysis) at Second Interim Analysis

Data cutoff date: 01 May 2024.

CARTITUDE-1

The efficacy of CARVYKTI was evaluated in CARTITUDE-1, an open-label, single-arm, multicenter trial in adult patients with relapsed or refractory multiple myeloma, who previously received at least 3 prior lines of therapy including a proteasome inhibitor, an immunomodulatory agent, and an anti-CD38 monoclonal antibody [see Adverse Reactions (6.1)] .

Patients with known active or prior history of significant central nervous system (CNS) disease, including CNS multiple myeloma, plasma cell leukemia, allogeneic stem cell transplant within 6 months before apheresis or ongoing treatment with immunosuppressants, creatinine clearance <40 mL/min, absolute lymphocyte concentration <300/µL, absolute neutrophil count <750 cells/mm^3, platelet count <50,000/mm^3, hepatic transaminases >3 times the upper limit of normal, cardiac ejection fraction <45%, or with active serious infection were excluded from the trial.

Of the 113 patients who underwent leukapheresis, 16 patients did not receive CARVYKTI due to progressive disease (n=2), death (n=9), or withdrawal from study (n=5). There were 97 patients in the efficacy evaluable population who received CARVYKTI, including 17 patients (18%) with manufacturing failures either because they received CARVYKTI that did not meet product release specifications for CARVYKTI or received CARVYKTI for which there were insufficient data to confirm product release specifications for CARVYKTI.

Of the 97 efficacy-evaluable patients, the median age was 61 years (range: 43 to 78 years), 59% were male, 71% were white, and 18% were black. Most patients (86%) were ISS Stage I or II. Of the 91 patients for whom baseline cytogenetic data were available, high-risk cytogenetics (presence of t(4:14), t(14:16), or 17p13 del) were present in 24% of patients. Thirteen percent of the patients had extramedullary disease.

The median number of prior lines of therapy was 6 (range: 3 to 18), with 82% of patients receiving 4 or more prior lines of therapy, 90% of patients had received prior autologous stem cell transplantation (ASCT) and 8% of patients received an allogeneic transplant. Ninety-nine percent of patients were refractory to their last line of prior therapy, and 88% were refractory to a proteasome inhibitor (PI), immunomodulatory agent, and anti-CD38 antibody.

Most patients (75%) treated with CARVYKTI received bridging therapy for control of their multiple myeloma during the manufacturing process. The median time from leukapheresis to product availability was 32 days (range: 27 to 66 days).

The most commonly used agents as bridging therapies (≥20% of patients) included dexamethasone: 62 patients (64%), bortezomib: 26 patients (27%), cyclophosphamide: 22 patients (23%), and pomalidomide: 21 patients (22%).

The efficacy results for CARTITUDE-1 Study are summarized in Table 9 below.

The major efficacy outcome measures were overall response rate, complete response rate and duration of response as assessed by the Independent Review Committee (IRC) using International Myeloma Working Group (IMWG) criteria (see Table 9). The median time to first response was 1 month (range: 0.9 to 10.7 months).

Table 9: Summary of efficacy results for CARTITUDE-1 based on IRC using IMWG criteria and duration of response results
 | CARVYKTI treated (N=97)
Overall Response Rate (sCR [All complete responses were stringent CRs.] + VGPR + PR) n (%) | 95 (97.9)
95% CI (%) | (92.7, 99.7)
Stringent complete response (sCR) n (%) | 78 (80.4)
95% CI [Exact 95% confidence interval.] (%) | (71.1, 87.8)
Very good partial response (VGPR) n (%) | 14 (14.4)
95% CI (%) | (8.1, 23.0)
Partial response (PR) n (%) | 3 (3.1)
95% CI (%) | (0.6, 8.8)
Duration of Response (DOR) [The estimated DOR rate was 60.3% (95% CI: 49.6%, 69.5%) at 24 months and 51.2% (95% CI: 39.0%, 62.1%) at 30 months.] | -
Number of responders DOR (Months):Median (95% CI) [Kaplan-Meier estimate.] | 95 NE (23.3, NE)
Number of responders with sCR DOR if best response is sCR (Months):Median (95% CI) | 78 NE (28.3, NE)
Number of responders with VGPR or better DOR if best response is VGPR or better (Months):Median (95% CI) | 92 NE (24.4, NE)
Notes: Based on a median duration of follow-up of 28 months.
CI=confidence interval; IRC=Independent Review Committee; IMWG=International Myeloma Working Group; NE=not estimable.

The IRC assessed overall response in the 113 patients that underwent leukapheresis was 84% (95% CI: 76, 90) with stringent CR rate of 69% (95% CI: 60, 77), VGPR rate of 12% (95% CI: 7, 20) and PR rate of 3% (95% CI: 1, 8).

15 REFERENCES

- DW, Santomasso BD, Locke FL, et al. ASTCT consensus grading for cytokine release syndrome and neurologic toxicity associated with immune effector cells. Biol Blood Marrow Transplant 2019; 25: 625–638.
- National Cancer Institute Common Terminology Criteria for Adverse Events (NCI CTCAE) v 5.0; 2017.

16 HOW SUPPLIED/STORAGE AND HANDLING

CARVYKTI®is supplied in one infusion bag containing a frozen suspension of genetically modified autologous T cells in 5% DMSO, either as a:

- 70 mL suspension in an infusion bag and metal cassette (NDC 57894-111-01)
  or
- 30 mL suspension in an infusion bag and metal cassette (NDC 57894-111-02)

Each CARVYKTI infusion bag is individually packed in an aluminum cryo-cassette.

Match the identity of the patient with the patient identifiers on the cassette and infusion bag upon receipt.

STORAGE AND HANDLING

Store and transport below -120 °C, e.g., in a container for cryogenic storage in the vapor phase of liquid nitrogen.

Store CARVYKTI in the original packaging containing the cassette protecting the infusion bag.

Thaw CARVYKTI prior to infusion [see Dosage and Administration (2)] .

17 PATIENT COUNSELING INFORMATION

Advise the patient to read the FDA-approved patient labeling (Medication Guide).

Inform patients of the risk of manufacturing failure [18%, (17/97 in the clinical study)]. In case of a manufacturing failure, a second manufacturing of CARVYKTI may be attempted. In addition, while the patient awaits the product, additional anticancer treatment (other than lymphodepletion) may be necessary and may increase the risk of adverse reactions during the pre-infusion period, which could delay or prevent the administration of CARVYKTI.

Advise patients that they will be monitored daily for the first 7 days following the infusion, and instruct patients to remain within proximity of a healthcare facility for at least 2 weeks following the infusion.

Prior to infusion, advise patients of the following risks and to seek immediate medical attention in the event of the following signs or symptoms:

Increased Early Mortality

Inform patients of the risk of early mortality. In a clinical study, treatment in the CARVYKTI arm was associated with a higher rate of death (14%) compared to the control arm (12%) in the first 10 months from randomization. This higher rate of death was observed before receiving CARVYKTI and after treatment with CARVYKTI. The reasons for death were progression of multiple myeloma and adverse events [see Warnings and Precautions (5.1), Clinical Studies (14)] .

Cytokine Release Syndrome (CRS)

Signs or symptoms of CRS, including fever, chills, fatigue, headache, tachycardia, hypotension, hypoxia, dizziness/lightheadedness or organ toxicities [see Warnings and Precautions (5.2), Adverse Reactions (6.1)].

Neurologic Toxicities

Signs or symptoms associated with neurologic events, some of which occur days, weeks or months following the infusion including [see Warnings and Precautions (5.3), Adverse Reactions (6.1)] :

ICANS:e.g., aphasia, encephalopathy, depressed level of consciousness, seizures, delirium, dysgraphia

Parkinsonism:e.g., tremor, micrographia, bradykinesia, rigidity, shuffling gait, stooped posture, masked facies, apathy, flat affect, lethargy, somnolence

Guillain Barré Syndrome:e.g., motor weakness and polyradiculoneuritis

Peripheral Neuropathy:e.g., peripheral motor and/or sensory nerve dysfunction

Cranial Nerve Palsies:e.g., facial paralysis, facial numbness

Prolonged and Recurrent Cytopenias

Signs or symptoms associated with bone marrow suppression including neutropenia, thrombocytopenia, anemia, or febrile neutropenia for several weeks or months. Signs or symptoms associated with bone marrow suppression may recur [see Warnings and Precautions (5.5), Adverse Reactions (6.1)] .

Infections

Signs or symptoms associated with infection [see Warnings and Precautions (5.6), Adverse Reactions (6.1)] .

Hypersensitivity Reactions

Signs or symptoms associated with hypersensitivity reactions including flushing, chest tightness, tachycardia, and difficulty breathing [see Warnings and Precautions (5.8)].

Immune Effector Cell-associated Enterocolitis

Signs or symptoms including persistent and severe diarrhea, abdominal pain and weight loss, post-infusion. Signs or symptoms of gastrointestinal perforation [see Warnings and Precautions (5.9)].

Secondary Malignancies

Secondary hematological malignancies, including myelodysplastic syndrome, acute myeloid leukemia, and T-cell malignancies (including in GI tract) have occurred [see Boxed Warning, Warnings and Precautions (5.10), Adverse Reactions (6.1, 6.2)].

Advise patients of the need to:

- Have periodic monitoring of blood counts before and after CARVYKTI infusion [see Warnings and Precautions (5.5)] .
- Contact Janssen Biotech, Inc. at 1-800-526-7736 if they are diagnosed with a secondary malignancy [see Warnings and Precautions (5.10)] .
- Avoid driving for at least 2 weeks [see Warnings and Precautions (5.3)] .
- Tell their physician about their treatment with CARVYKTI before receiving a live virus vaccine [see Warnings and Precautions (5.7)] .

Manufactured/Marketed by:
Janssen Biotech, Inc.
Horsham, PA 19044, USA
U.S. License Number 1864

Marketed by:
Legend Biotech
Somerset, NJ 08873, USA

For patent information: www.janssenpatents.com
© Johnson & Johnson and its affiliates 2022–2025

MEDICATION GUIDE
CARVYKTI®(car-vick-tee)
(ciltacabtagene autoleucel)

Read this Medication Guide before you start your CARVYKTI treatment. The more you know about your treatment, the more active you can be in your care. Talk with your healthcare provider if you have questions about your health condition or treatment. Reading this Medication Guide does not take the place of talking with your healthcare provider about your treatment.

What is the most important information I should know about CARVYKTI?
CARVYKTI may cause side effects that are severe or life-threatening and can lead to death. Call your healthcare provider or get emergency help right away if you get any of the following:

- fever (100.4 °F/38 °C or higher)
- chills or shaking chills
- fast or irregular heartbeat
- difficulty breathing
- very low blood pressure
- dizziness/light headedness
- persistent or severe diarrhea, abdominal pain and weight loss following CARVYKTI infusion
- effects on your nervous system, some of which can occur days or weeks after you receive the infusion, and may initially be subtle such as:
  - feeling confused, less alert, or disoriented, having difficulty speaking or slurred speech, having difficulty reading, writing, and understanding words, memory loss
  - loss of coordination affecting movement and balance, slower movements, changes in handwriting
  - personality changes including a reduced ability to express emotions, being less talkative, disinterest in activities, and reduced facial expression
  - tingling, numbness, and pain of hands and feet, difficulty walking, leg and/or arm weakness, and difficulty breathing
  - facial numbness, difficulty moving muscles of face and eyes

It is important that you tell your healthcare providers that you have received CARVYKTI and to show them your CARVYKTI Patient Wallet Card. Your healthcare providers may give you other medicines to treat your side effects.

What is CARVYKTI?

- CARVYKTI is a treatment used for adult patients who have cancer of the bone marrow called multiple myeloma. It is used when at least one other treatment has not worked or has stopped working.
- CARVYKTI is a medicine made from your own white blood cells, which have been changed (genetically modified) to recognize and attack your multiple myeloma cells.

Before you receive CARVYKTI tell your healthcare provider about all your medical conditions, including if you have:

- Current or past neurologic problems (such as seizures, stroke, new or worsening memory loss)
- Lung or breathing problems
- Heart problems
- Liver problems
- Kidney problems
- A recent or active infection
- Low blood counts

Tell your healthcare provider about all the medicines you take,including prescription and over-the-counter medicines, vitamins, and herbal supplements.

How will I receive CARVYKTI?

- CARVYKTI is made from your own white blood cells, so your blood will be collected by a process called 'leukapheresis' (loo-kah-fur-ee-sis). The procedure can take 3 to 6 hours and may need to be repeated.
- Your white blood cells are sent to a manufacturing center to make CARVYKTI. It takes about 4–5 weeks from the time your cells are received at the manufacturing site and are available to be shipped back to your healthcare provider, but the time may vary.
- While CARVYKTI is being made you may get other medicines to treat the multiple myeloma. This is so that your multiple myeloma does not get worse.

Before you get CARVYKTI, your healthcare provider will give you chemotherapy for 3 days to prepare your body.
30 to 60 minutes before you are given CARVYKTI, you may be given other medicines. These may include:

- medicines for an allergic reaction (antihistamines)
- medicines for fever (such as acetaminophen)

When your CARVYKTI is ready, your healthcare provider will give CARVYKTI to you through a catheter (tube) placed into your vein (intravenous infusion). Your dose of CARVYKTI will be given in one infusion bag. The infusion usually takes approximately 30–60 minutes.
After getting CARVYKTI,you will be monitored daily for at least 7 days after the infusion.
You should plan to stay close to a healthcare facility for at least 2 weeks. Your healthcare provider will check to see that your treatment is working and help you with any side effects that may occur. You may be hospitalized if you develop serious side effects until your side effects are under control and it is safe for you to leave the hospital.
Your healthcare provider will want to do blood tests to follow your progress. It is important that you have your blood tested. If you miss an appointment, call your healthcare provider as soon as possible to reschedule.

What should I avoid after receiving CARVYKTI?

- Avoid driving for at least 2 weeks after you get CARVYKTI.
- You must not be given certain vaccines called live vaccines for some time before and after CARVYKTI treatment. Talk to your healthcare provider if you need to have any vaccinations.
- Do not donate blood, organs, tissues, or cells for transplantation.

What are the possible or reasonably likely side effects of CARVYKTI?
The most common side effects of CARVYKTI include:

- fever (100.4 °F/38 °C or higher), chills
- dizziness or light-headedness
- headache, muscle or joint pain, feeling very tired
- altered mental state, confusion
- infections
- low levels of antibodies (immunoglobulins) in the blood
- cough, being short of breath
- diarrhea, nausea, decreased appetite, constipation
- fast or irregular heartbeat
- problems with blood clotting

In a study comparing CARVYKTI to standard therapy, there was a higher rate of death in the first 10 months in the CARVYKTI arm (14%) compared to the standard therapy arm (12%). The increased rate of deaths occurred before receiving CARVYKTI and after treatment with CARVYKTI. The reasons for death were progression of multiple myeloma and side effects of the treatment.
CARVYKTI can cause a very common side effect called cytokine release syndrome or CRS, which can be severe or fatal. Symptoms of CRS include fever, difficulty breathing, dizziness or lightheadedness, nausea, headache, fast heartbeat, low blood pressure, or fatigue. Tell your healthcare provider right away if you develop fever or any of these other symptoms after receiving CARVYKTI.
CARVYKTI can increase the risk of life-threatening infections including COVID-19 that may lead to death. Tell your healthcare provider right away if you develop fever, chills, or any signs or symptoms of an infection.
CARVYKTI can cause various neurologic side effects, some of which may be severe or fatal. Symptoms include but are not limited to confusion, disorientation, loss of consciousness, seizures, difficulty speaking, reading or writing, tremor, slower movements, changes in personality, depression, tingling and numbness of hands and feet, leg and arm weakness, and facial numbness.
CARVYKTI can lower one or more types of your blood cells (red blood cells, white blood cells, or platelets [cells that help blood to clot]), which may make you feel weak or tired or increase your risk of severe infection or bleeding that may lead to death. After treatment, your healthcare provider will test your blood to check for this. Tell your healthcare provider right away if you get a fever, chills, or any signs or symptoms of an infection, are feeling tired, or have bruising or bleeding.
CARVYKTI can cause serious gastrointestinal side effects, including severe or persistent diarrhea or ruptured bowel, which can be life-threatening and may lead to death. Tell your healthcare provider right away if you develop diarrhea, abdominal pain, weight loss, fever, chills, or any signs or symptoms of an infection.
CARVYKTI may increase your risk of getting cancers including certain types of blood cancers. Your healthcare provider should monitor you for this.
Having CARVYKTI in your blood may cause some commercial Human Immunodeficiency Virus (HIV) tests to incorrectly give you an HIV-positive result even though you may be HIV-negative.
These are not all the possible side effects of CARVYKTI. Call your healthcare provider if you have any side effects.
You may report side effects to FDA at 1-800-FDA-1088.

General information about the safe and effective use of CARVYKTI
Medicines are sometimes prescribed for purposes other than those listed in a Medication Guide. If you would like more information about CARVYKTI, talk with your healthcare provider. You can ask your healthcare provider for information about CARVYKTI that is written for health professionals. For more information go to www.CARVYKTI.com or call 1-800-526-7736.

What are the ingredients in CARVYKTI?
Active ingredient: ciltacabtagene autoleucel
Inactive ingredients:DMSO

Manufactured/Marketed by: Janssen Biotech, Inc., Horsham, PA 19044, USA. U.S. License Number 1864

Marketed by: Legend Biotech, Somerset, NJ 08873, USA. For patent information: www.janssenpatents.com.

For more information, call 1-800-526-7736 or go to www.CARVYKTI.com.

© Johnson & Johnson and its affiliates 2022–2025

This Medication guide has been approved by the U.S. Food and Drug Administration.

Revised: October 2025

PRINCIPAL DISPLAY PANEL - 70 mL Bag Label

ciltacabtagene autoleucel
CARVYKTI™
Suspension for Intravenous Infusion

NDC 57894-111-01

Dose: One sterile bag for infusion.

Contents: A maximum of 1x10^8CAR-positive viable T cells in a 70 mL frozen suspension per
patient-specific infusion bag, containing 5% DMSO.

FOR AUTOLOGOUS USE ONLY.
FOR INTRAVENOUS USE ONLY.

Dosage: See Prescribing Information.

Storage: Store and transport in a vapor phase of
liquid nitrogen ≤ -120°C (-184°F). Thaw before using.

DO NOT re-freeze or refrigerate once thawed.
DO NOT irradiate.
DO NOT use a leukodepleting filter.

CULTURED, GENETICALLY MODIFIED.
NO U.S. STANDARD OF POTENCY.
NOT EVALUATED FOR INFECTIOUS SUBSTANCES.

NO PRESERVATIVE

Attention: Dispense the enclosed Medication
Guide to each patient.

Rx only

One Sterile Bag for Infusion

Mfg./Mktd. by: Janssen Biotech, Inc., Horsham,
PA 19044, USA; U.S. License No. 1864

Mktd. by: Legend Biotech, Somerset, NJ 08873, USA

Upon receipt: Match the identity of
the patient with the patient
identifiers on the cassette and
infusion bag.

BAG ID: COI [followed by Bag Number]
LOT: XXXXXXXX
EXP: YYYY-MMM-DD

ORDER ID:

PATIENT
NAME:

DOB: YYYY-MMM-DD

MEDICAL RECORD NO.:

DIN:

© 2022 Janssen
10579200

LEGEND
BIOTECH

janssen

PRINCIPAL DISPLAY PANEL - 30 mL Bag Label

ciltacabtagene autoleucel
CARVYKTI™
Suspension for Intravenous Infusion

NDC 57894-111-02

Dose: One sterile bag for infusion.

Contents: A maximum of 1x10^8CAR-positive viable T cells in a 30 mL frozen suspension per
patient-specific infusion bag, containing 5% DMSO.

FOR AUTOLOGOUS USE ONLY.
FOR INTRAVENOUS USE ONLY.

Dosage: See Prescribing Information.

Storage: Store and transport in a vapor phase of
liquid nitrogen ≤ -120°C (-184°F). Thaw before using.

DO NOT re-freeze or refrigerate once thawed.
DO NOT irradiate.
DO NOT use a leukodepleting filter.

CULTURED, GENETICALLY MODIFIED.
NO U.S. STANDARD OF POTENCY.
NOT EVALUATED FOR INFECTIOUS SUBSTANCES.

NO PRESERVATIVE

Attention: Dispense the enclosed Medication
Guide to each patient.

Rx only

One Sterile Bag for Infusion

Mfg./Mktd. by: Janssen Biotech, Inc., Horsham,
PA 19044, USA; U.S. License No. 1864

Mktd. by: Legend Biotech, Somerset, NJ 08873, USA

Upon receipt: Match the identity of
the patient with the patient
identifiers on the cassette and
infusion bag.

BAG ID: COI [followed by Bag Number]
LOT: XXXXXXXX
EXP: YYYY-MMM-DD

ORDER ID:

PATIENT
NAME:

DOB: YYYY-MMM-DD

MEDICAL RECORD NO.:

DIN:

© 2022 Janssen
10580600

LEGEND
BIOTECH

janssen